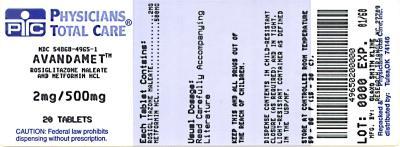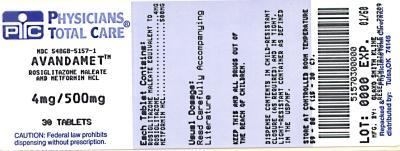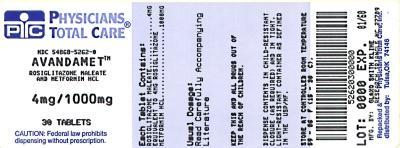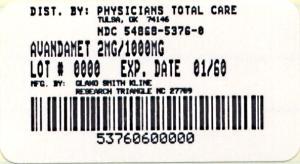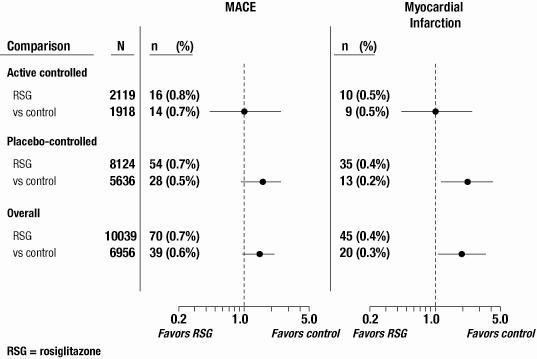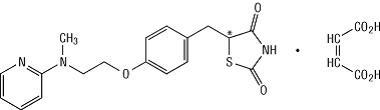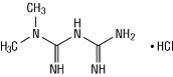 DRUG LABEL: AVANDAMET
                
NDC: 54868-4965 | Form: TABLET, FILM COATED
Manufacturer: Physicians Total Care, Inc.
Category: prescription | Type: HUMAN PRESCRIPTION DRUG LABEL
Date: 20120830

ACTIVE INGREDIENTS: ROSIGLITAZONE MALEATE 2 mg/1 1; METFORMIN HYDROCHLORIDE 500 mg/1 1
INACTIVE INGREDIENTS: HYPROMELLOSE 2910 (3 MPA.S); LACTOSE MONOHYDRATE; MAGNESIUM STEARATE; CELLULOSE, MICROCRYSTALLINE; POLYETHYLENE GLYCOL 400; POVIDONE K29/32; SODIUM STARCH GLYCOLATE TYPE A POTATO; TITANIUM DIOXIDE; FERRIC OXIDE RED; FERRIC OXIDE YELLOW

HIGHLIGHTS OF PRESCRIBING INFORMATION

These highlights do not include all the information needed to use AVANDAMET safely and effectively. See full prescribing information for AVANDAMET.
AVANDAMET (rosiglitazone maleate and metformin hydrochloride) Tablets
Initial U.S. Approval: 2002

RECENT MAJOR CHANGES

Boxed Warning | 02/2011
Indications and Usage (1) | 02/2011
Dosage and Administration (2) | 02/2011
Warnings and Precautions, Cardiac Failure (5.2) | 02/2011
Warnings and Precautions, Major Adverse Cardiovascular Events (5.3) | 02/2011
Warnings and Precautions, Fractures (5.8) | 02/2011

WARNINGS

See full prescribing information for complete boxed warning.

Rosiglitazone maleate: CONGESTIVE HEART FAILURE AND MYOCARDIAL INFARCTION

- Thiazolidinediones, including rosiglitazone, cause or exacerbate heart failure in some patients (5.2). After initiation of AVANDAMET, and after dose increases, observe patients carefully for signs and symptoms of heart failure (including excessive, rapid weight gain, dyspnea, and/or edema). If these signs and symptoms develop, the heart failure should be managed according to current standards of care. Furthermore, discontinuation or dose reduction must be considered. (5.2)
- AVANDAMET is not recommended in patients with symptomatic heart failure. Initiation of AVANDAMET in patients with established NYHA Class III or IV heart failure is contraindicated. (4, 5.2)
- A meta-analysis of 52 clinical trials (mean duration 6 months; 16,995 total patients), most of which compared rosiglitazone to placebo, showed rosiglitazone to be associated with a statistically significant increased risk of myocardial infarction. Three other trials (mean duration 46 months; 14,067 total patients), comparing rosiglitazone to some other approved oral antidiabetic agents or placebo, showed a statistically non-significant increased risk of myocardial infarction and a statistically non-significant decreased risk of death. There have been no clinical trials directly comparing cardiovascular risk of rosiglitazone and ACTOS® (pioglitazone, another thiazolidinedione), but in a separate trial, pioglitazone (when compared to placebo) did not show an increased risk of myocardial infarction or death. (5.3)

Metformin hydrochloride: LACTIC ACIDOSIS

- Lactic acidosis can occur due to metformin accumulation. The risk increases with conditions such as sepsis, dehydration, excess alcohol intake, hepatic insufficiency, renal impairment and acute congestive heart failure. (5.1)
- Symptoms include malaise, myalgias, respiratory distress, increasing somnolence and nonspecific abdominal distress. Laboratory abnormalities include low pH, increased anion gap and elevated blood lactate. (5.1)
- If acidosis is suspected, discontinue AVANDAMET and hospitalize the patient immediately. (5.1)

1 INDICATIONS AND USAGE

AVANDAMET is a combination antidiabetic product containing a thiazolidinedione and a biguanide. After consultation with a healthcare professional who has considered and advised the patient of the risks and benefits of rosiglitazone, this drug is indicated as an adjunct to diet and exercise to improve glycemic control when treatment with both rosiglitazone and metformin is appropriate in adults with type 2 diabetes mellitus who either are:

- already taking rosiglitazone, or
- not already taking rosiglitazone and are unable to achieve glycemic control on other diabetes medications and, in consultation with their healthcare provider, have decided not to take pioglitazone (ACTOS) or pioglitazone-containing products (ACTOPLUS MET®, ACTOPLUS MET XR®, DUETACT®) for medical reasons. (1)

Other Important Limitations of Use:

- Should not be used in patients with type 1 diabetes or for the treatment of diabetic ketoacidosis. (1)
- Coadministration with insulin is not recommended. (1, 5.2, 5.3)

2 DOSAGE AND ADMINISTRATION

- Individualize the starting dose based on the patient’s current regimen. (2.1)
- Dose increases should be accompanied by careful monitoring for adverse events related to fluid retention. (2.1)
- Give in divided doses with meals with gradual dose escalation to reduce the gastrointestinal side effects. (2.2)
- Do not exceed the maximum recommended daily dose of 8 mg rosiglitazone and 2,000 mg metformin. (2.3)
- Do not initiate if the patient exhibits clinical evidence of active liver disease or increased serum transaminase levels. (2.4)

3 DOSAGE FORMS AND STRENGTHS

Oval, film-coated tablets containing rosiglitazone/metformin hydrochloride: 2 mg/500 mg, 4 mg/500 mg, 2 mg/1,000 mg, and 4 mg/1,000 mg (3)

4 CONTRAINDICATIONS

- Initiation in patients with established NYHA Class III or IV heart failure. (4)
- Use in significant renal disease or renal dysfunction. (4)
- Use in acute or chronic metabolic acidosis. (4)
- Use in patients undergoing radiologic studies involving intravascular administration of iodinated contrast materials. (4, 5.1)

5 WARNINGS AND PRECAUTIONS

- Fluid retention, which may exacerbate or lead to heart failure, may occur. Combination use with insulin and use in congestive heart failure NYHA Class I and II may increase risk of other cardiovascular effects. (5.2)
- Increased risk of myocardial infarction has been observed in a meta-analysis of 52 clinical trials of rosiglitazone (incidence rate 0.4% versus 0.3%). (5.3)
- Coadministration with insulin is not recommended. (1, 5.2, 5.3)
- Assess renal function before starting therapy and at least annually. (5.1)
- Avoid use in patients with evidence of hepatic disease. (2.4, 5.1)
- Warn patients against excessive alcohol intake. (5.1)
- Promptly evaluate patients who develop laboratory abnormalities or clinical illness for evidence of ketoacidosis or lactic acidosis. (5.1)
- Dose-related edema (5.4), weight gain (5.5), and anemia (5.9) may occur.
- Macular edema has been reported. (5.7)
- Increased incidence of bone fracture. (5.8)
- Measure hematologic parameters annually. (5.9)

6 ADVERSE REACTIONS

The most common adverse reactions (≥10%) include nausea/vomiting, diarrhea, headache, and dyspepsia. (6.1)

To report SUSPECTED ADVERSE REACTIONS, contact GlaxoSmithKline at 1-888-825-5249 or FDA at 1-800-FDA-1088 or www.fda.gov/medwatch.

7 DRUG INTERACTIONS

- Inhibitors of CYP2C8 (e.g., gemfibrozil) may increase rosiglitazone levels. (7.1)
- Inducers of CYP2C8 (e.g., rifampin) may decrease rosiglitazone levels. (7.1)
- Cationic drugs eliminated by renal tubular secretion; use with caution. (7.2)

8 USE IN SPECIFIC POPULATIONS

- Do not use during pregnancy. No human or animal data. (8.1)
- Safety and effectiveness in children under 18 years have not been established. (8.4)
- Because reduced renal function is associated with increasing age, use with caution in elderly patients. (8.5)

FULL PRESCRIBING INFORMATION

WARNINGS

Rosiglitazone maleate: CONGESTIVE HEART FAILURE AND MYOCARDIAL INFARCTION

- Thiazolidinediones, including rosiglitazone, cause or exacerbate congestive heart failure in some patients [see Warnings and Precautions (5.2)]. After initiation of AVANDAMET, and after dose increases, observe patients carefully for signs and symptoms of heart failure (including excessive, rapid weight gain, dyspnea, and/or edema). If these signs and symptoms develop, the heart failure should be managed according to current standards of care. Furthermore, discontinuation or dose reduction of AVANDAMET must be considered.
- AVANDAMET is not recommended in patients with symptomatic heart failure. Initiation of AVANDAMET in patients with established NYHA Class III or IV heart failure is contraindicated. [See Contraindications (4) and Warnings and Precautions (5.2).]
- A meta-analysis of 52 clinical trials (mean duration 6 months; 16,995 total patients), most of which compared rosiglitazone to placebo, showed rosiglitazone to be associated with an increased risk of myocardial infarction. Three other trials (mean duration 46 months; 14,067 total patients), comparing rosiglitazone to some other approved oral antidiabetic agents or placebo, showed a statistically non-significant increased risk of myocardial infarction, and a statistically non-significant decreased risk of death. There have been no clinical trials directly comparing cardiovascular risk of rosiglitazone and ACTOS® (pioglitazone, another thiazolidinedione), but in a separate trial, pioglitazone (when compared to placebo) did not show an increased risk of myocardial infarction or death. [See Warnings and Precautions (5.3).]

Metformin hydrochloride: LACTIC ACIDOSIS

- Lactic acidosis is a rare, but serious complication that can occur due to metformin accumulation. The risk increases with conditions such as sepsis, dehydration, excess alcohol intake, hepatic insufficiency, renal impairment, and acute congestive heart failure. [See Warnings and Precautions (5.1).]
- Symptoms include malaise, myalgias, respiratory distress, increasing somnolence, and nonspecific abdominal distress. Laboratory abnormalities include low pH, increased anion gap and elevated blood lactate. [See Warnings and Precautions (5.1).]
- If acidosis is suspected, discontinue AVANDAMET and hospitalize the patient immediately [see Warnings and Precautions (5.1)].

1 INDICATIONS AND USAGE

After consultation with a healthcare professional who has considered and advised the patient of the risks and benefits of rosiglitazone, AVANDAMET® is indicated as an adjunct to diet and exercise to improve glycemic control when treatment with both rosiglitazone and metformin is appropriate in adults with type 2 diabetes mellitus who either are:

- already taking rosiglitazone, or
- not already taking rosiglitazone and unable to achieve glycemic control on other diabetes medications and, in consultation with their healthcare provider, have decided not to take pioglitazone (ACTOS®) or pioglitazone-containing products (ACTOPLUS MET®, ACTOPLUS MET XR®, DUETACT®) for medical reasons.

Other Important Limitations of Use:

- Due to its mechanism of action, rosiglitazone is active only in the presence of endogenous insulin. Therefore, AVANDAMET should not be used in patients with type 1 diabetes.
- Coadministration of AVANDAMET with insulin is not recommended [see Warnings and Precautions (5.2, 5.3)].

2 DOSAGE AND ADMINISTRATION

Prior to prescribing AVANDAMET, refer to Indications and Usage (1) for appropriate patient selection.

2.1 Starting Dose

AVANDAMET is generally given in divided doses with meals.

All patients should start the rosiglitazone component of AVANDAMET at the lowest recommended dose. Further increases in the dose of rosiglitazone should be accompanied by careful monitoring for adverse events related to fluid retention [see Boxed Warning and Warnings and Precautions (5.4)].

If therapy with a combination tablet containing rosiglitazone and metformin is considered appropriate for a patient with type 2 diabetes mellitus, then the selection of the dose of AVANDAMET should be based on the patient’s current doses of rosiglitazone and/or metformin.

To switch to AVANDAMET for patients currently treated with metformin, the usual starting dose of AVANDAMET is 4 mg rosiglitazone (total daily dose) plus the dose of metformin already being taken (see Table 1).

To switch to AVANDAMET for patients currently treated with rosiglitazone, the usual starting dose of AVANDAMET is 1,000 mg metformin (total daily dose) plus the dose of rosiglitazone already being taken (see Table 1).

When switching from combination therapy of rosiglitazone plus metformin as separate tablets, the usual starting dose of AVANDAMET is the dose of rosiglitazone and metformin already being taken.

Table 1. AVANDAMET Starting Dose for Patients Treated with Metformin and/or Rosiglitazone
PRIOR THERAPY | Usual AVANDAMET Starting Dose
Total daily dose | Tablet strength | Number of tablets
Metformina
1,000 mg/day | 2 mg/500 mg | 1 tablet twice a day
2,000 mg/day | 2 mg/1,000 mg | 1 tablet twice a day
Rosiglitazone
4 mg/day | 2 mg/500 mg | 1 tablet twice a day
8 mg/day | 4 mg/500 mg | 1 tablet twice a day

aFor patients on doses of metformin between 1,000 and 2,000 mg/day, initiation of AVANDAMET requires individualization of therapy.

2.2 Dose Titration

AVANDAMET is generally given in divided doses with meals, with gradual dose escalation. This reduces gastrointestinal side effects (largely due to metformin) and permits determination of the minimum effective dose for the individual patient.

Sufficient time should be given to assess adequacy of therapeutic response. FPG should be used initially to determine the therapeutic response to AVANDAMET. If additional glycemic control is needed, the daily dose of AVANDAMET may be increased by increments of 4 mg rosiglitazone and/or 500 mg metformin.

After an increase in metformin dosage, dose titration is recommended if patients are not adequately controlled after 1 to 2 weeks. After an increase in rosiglitazone dosage, dose titration is recommended if patients are not adequately controlled after 8 to 12 weeks.

2.3 Maximum Dose

The maximum recommended total daily dose of AVANDAMET is 8 mg rosiglitazone (taken as 4 mg twice daily) and 2,000 mg metformin (taken as 1,000 mg twice daily).

2.4 Specific Patient Populations

Renal Impairment: Any dosage adjustment should be based on a careful assessment of renal function. Generally, elderly, debilitated, and malnourished patients should not be titrated to the maximum dose of AVANDAMET. Monitoring of renal function is necessary to aid in prevention of metformin-associated lactic acidosis, particularly in the elderly [see Warnings and Precautions (5.1)].

Hepatic Impairment: Liver enzymes should be measured prior to initiating treatment with AVANDAMET. Therapy with AVANDAMET should not be initiated if the patient exhibits clinical evidence of active liver disease or increased serum transaminase levels (ALT >2.5X upper limit of normal at start of therapy). After initiation of AVANDAMET, liver enzymes should be monitored periodically per the clinical judgment of the healthcare professional [see Warnings and Precautions (5.6) and Clinical Pharmacology (12.3)].

Geriatric: The initial and maintenance dosing of AVANDAMET should be conservative in patients with advanced age, due to the potential for decreased renal function in this population.

Pediatric: Safety and effectiveness of AVANDAMET in pediatric patients have not been established. AVANDAMET and rosiglitazone are not recommended for use in pediatric patients.

Pregnancy: AVANDAMET is not recommended for use in pregnancy.

3 DOSAGE FORMS AND STRENGTHS

Each film-coated oval tablet contains rosiglitazone as the maleate and metformin hydrochloride as follows:

- 2 mg/500 mg – pale pink, debossed with gsk on one side and 2/500 on the other
- 4 mg/500 mg – orange, debossed with gsk on one side and 4/500 on the other
- 2 mg/1,000 mg – yellow, debossed with gsk on one side and 2/1000 on the other
- 4 mg/1,000 mg – pink, debossed with gsk on one side and 4/1000 on the other

4 CONTRAINDICATIONS

- Initiation in patients with established New York Heart Association (NYHA) Class III or IV heart failure [see Boxed Warning].
- Use in patients with renal disease or renal dysfunction (e.g., as suggested by serum creatinine levels ≥1.5 mg/dL [males], ≥1.4 mg/dL [females], or abnormal creatinine clearance), which may also result from conditions such as cardiovascular collapse (shock), acute myocardial infarction, and septicemia [see Warnings and Precautions (5.1)].
- Use in patients with acute or chronic metabolic acidosis, including diabetic ketoacidosis, with or without coma.
- Use in patients undergoing radiologic studies involving intravascular administration of iodinated contrast materials, because use of such products may result in acute alteration of renal function. AVANDAMET should be temporarily discontinued in these patients. [See Warnings and Precautions (5.1).]

5 WARNINGS AND PRECAUTIONS

5.1 Lactic Acidosis

Incidence and Management: Lactic acidosis is a rare, but serious, metabolic complication that can occur due to metformin accumulation during treatment with AVANDAMET; when it occurs, it is fatal in approximately 50% of cases. Lactic acidosis may also occur in association with a number of pathophysiologic conditions, including diabetes mellitus, and whenever there is significant tissue hypoperfusion and hypoxemia. Lactic acidosis is characterized by elevated blood lactate levels (>5 mmol/L), decreased blood pH, electrolyte disturbances with an increased anion gap, and an increased lactate/pyruvate ratio. When metformin is implicated as the cause of lactic acidosis, metformin plasma levels >5 mcg/mL are generally found.

The reported incidence of lactic acidosis in patients receiving metformin is very low (approximately 0.03 cases/1,000 patient years of exposure, with approximately 0.015 fatal cases/1,000 patient years of exposure). Reported cases have occurred primarily in diabetic patients with significant renal insufficiency, including both intrinsic renal disease and renal hypoperfusion, often in the setting of multiple concomitant medical/surgical problems and multiple concomitant medications. Patients with congestive heart failure requiring pharmacologic management, in particular those with unstable or acute congestive heart failure who are at risk of hypoperfusion and hypoxemia, are at increased risk of lactic acidosis. The risk of lactic acidosis increases with the degree of renal dysfunction and the patient's age. The risk of lactic acidosis may, therefore, be significantly decreased by regular monitoring of renal function in patients taking AVANDAMET and by use of the minimum effective dose of AVANDAMET. In particular, treatment of the elderly should be accompanied by careful monitoring of renal function. Treatment with AVANDAMET should not be initiated in patients ≥80 years of age unless measurement of creatinine clearance demonstrates that renal function is not reduced, as these patients are more susceptible to developing lactic acidosis. In addition, AVANDAMET should be promptly withheld in the presence of any condition associated with hypoxemia, dehydration, or sepsis. Because impaired hepatic function may significantly limit the ability to clear lactate, AVANDAMET should generally be avoided in patients with clinical or laboratory evidence of hepatic disease. Patients should be cautioned against excessive alcohol intake, either acute or chronic, when taking AVANDAMET, since alcohol potentiates the effects of metformin on lactate metabolism. In addition, AVANDAMET should be temporarily discontinued prior to any intravascular radiocontrast study and for any surgical procedure.

The onset of lactic acidosis often is subtle, and accompanied only by nonspecific symptoms such as malaise, myalgias, respiratory distress, increasing somnolence, and nonspecific abdominal distress. There may be associated hypothermia, hypotension, and resistant bradyarrhythmias with more marked acidosis. The patient and the patient's physician must be aware of the possible importance of such symptoms and the patient should be instructed to notify the physician immediately if they occur. AVANDAMET should be withdrawn until the situation is clarified. Serum electrolytes, ketones, blood glucose and, if indicated, blood pH, lactate levels, and even blood metformin levels may be useful. Once a patient is stabilized on any dose level of AVANDAMET, gastrointestinal symptoms, which are common during initiation of therapy, are unlikely to be drug related. Later occurrence of gastrointestinal symptoms could be due to lactic acidosis or other serious disease.

Levels of fasting venous plasma lactate above the upper limit of normal but less than 5 mmol/L in patients taking AVANDAMET do not necessarily indicate impending lactic acidosis and may be explainable by other mechanisms, such as poorly controlled diabetes or obesity, vigorous physical activity or technical problems in sample handling.

Lactic acidosis should be suspected in any diabetic patient with metabolic acidosis lacking evidence of ketoacidosis (ketonuria and ketonemia).

Lactic acidosis is a medical emergency that must be treated in a hospital setting. In a patient with lactic acidosis who is taking AVANDAMET, the drug should be discontinued immediately and general supportive measures promptly instituted. Because metformin is dialyzable (with a clearance of up to 170 mL/min under good hemodynamic conditions), prompt hemodialysis is recommended to correct the acidosis and remove the accumulated metformin. Such management often results in prompt reversal of symptoms and recovery [see Contraindications (4)].

Factors That May Predispose Patients to Lactic Acidosis: Assessment of Renal Function: Metformin is known to be substantially excreted by the kidney, and the risk of metformin accumulation and lactic acidosis increases with the degree of impairment of renal function. Thus, patients with serum creatinine levels above the upper limit of normal for their age should not receive AVANDAMET. In patients with advanced age, AVANDAMET should be carefully titrated to establish the minimum dose for adequate glycemic effect, because aging is associated with reduced renal function. [See Dosage and Administration (2.4) and Use in Specific Populations (8.5).]

Before initiation of therapy with AVANDAMET and at least annually thereafter, renal function should be assessed and verified as normal. In patients in whom development of renal dysfunction is anticipated, renal function should be assessed more frequently and AVANDAMET discontinued if evidence of renal impairment is present.

Medications That Affect Renal Function: Concomitant medication(s) that may affect renal function or result in significant hemodynamic change or may interfere with the disposition of metformin, such as cationic drugs that are eliminated by renal tubular secretion [see Drug Interactions (7.2) and Clinical Pharmacology (12.4)], should be used with caution.

Hypoxic States: Cardiovascular collapse (shock) from whatever cause, acute congestive heart failure, acute myocardial infarction, and other conditions characterized by hypoxemia have been associated with lactic acidosis and may also cause prerenal azotemia. When such events occur in patients receiving AVANDAMET, the drug should be promptly discontinued.

Radiologic Studies With Intravascular Iodinated Contrast Materials: Intravascular contrast studies with iodinated materials can lead to acute alteration of renal function and have been associated with lactic acidosis in patients receiving metformin [see Contraindications (4)]. Therefore, in patients in whom any such study is planned, AVANDAMET should be temporarily discontinued at the time of or prior to the procedure, and withheld for 48 hours subsequent to the procedure and reinstituted only after renal function has been re-evaluated and found to be normal.

Surgical Procedures: Use of AVANDAMET should be temporarily suspended for any surgical procedure (except minor procedures not associated with restricted intake of food and fluids) and should not be restarted until the patient's oral intake has resumed and renal function has been evaluated as normal.

Alcohol Intake: Alcohol potentiates the effect of metformin on lactate metabolism. Patients, therefore, should be warned against excessive alcohol intake, acute or chronic, while receiving AVANDAMET.

Change in Clinical Status of Patients With Previously Controlled Diabetes: A patient with type 2 diabetes previously well-controlled on AVANDAMET who develops laboratory abnormalities or clinical illness (especially vague and poorly defined illness) should be evaluated promptly for evidence of ketoacidosis or lactic acidosis. Evaluation should include serum electrolytes and ketones, blood glucose and, if indicated, blood pH, lactate, pyruvate, and metformin levels. If acidosis of either form occurs, AVANDAMET must be stopped immediately and other appropriate corrective measures initiated.

[See also Warnings and Precautions (5.6).]

5.2 Cardiac Failure

Rosiglitazone, like other thiazolidinediones, alone or in combination with other antidiabetic agents, can cause fluid retention, which may exacerbate or lead to heart failure. Patients should be observed for signs and symptoms of heart failure. If these signs and symptoms develop, the heart failure should be managed according to current standards of care. Furthermore, discontinuation or dose reduction of rosiglitazone must be considered [see Boxed Warning].

Patients with congestive heart failure (CHF) NYHA Class I and II treated with rosiglitazone have an increased risk of cardiovascular events. A 52-week, double-blind, placebo-controlled echocardiographic trial was conducted in 224 patients with type 2 diabetes mellitus and NYHA Class I or II CHF (ejection fraction ≤45%) on background antidiabetic and CHF therapy. An independent committee conducted a blinded evaluation of fluid-related events (including congestive heart failure) and cardiovascular hospitalizations according to predefined criteria (adjudication). Separate from the adjudication, other cardiovascular adverse events were reported by investigators. Although no treatment difference in change from baseline of ejection fractions was observed, more cardiovascular adverse events were observed with rosiglitazone treatment compared to placebo during the 52-week trial. (See Table 2.)

Table 2. Emergent Cardiovascular Adverse Events in Patients With Congestive Heart Failure (NYHA Class I and II) Treated With Rosiglitazone or Placebo (in Addition to Background Antidiabetic and CHF Therapy)
Events | Rosiglitazone | Placebo
 | N = 110; n (%) | N = 114; n (%)
Adjudicated
Cardiovascular deaths | 5 (5%) | 4 (4%)
CHF worsening | 7 (6%) | 4 (4%)
– with overnight hospitalization | 5 (5%) | 4 (4%)
– without overnight hospitalization | 2 (2%) | 0 (0%)
New or worsening edema | 28 (25%) | 10 (9%)
New or worsening dyspnea | 29 (26%) | 19 (17%)
Increases in CHF medication | 36 (33%) | 20 (18%)
Cardiovascular hospitalizationa | 21 (19%) | 15 (13%)
Investigator-reported, non-adjudicated
Ischemic adverse events | 10 (9%) | 5 (4%)
– Myocardial infarction | 5 (5%) | 2 (2%)
– Angina | 6 (5%) | 3 (3%)

aIncludes hospitalization for any cardiovascular reason.

Initiation of AVANDAMET in patients with established NYHA Class III or IV heart failure is contraindicated. AVANDAMET is not recommended in patients with symptomatic heart failure. [See Boxed Warning.]

Patients experiencing acute coronary syndromes have not been studied in controlled clinical trials. In view of the potential for development of heart failure in patients having an acute coronary event, initiation of AVANDAMET is not recommended for patients experiencing an acute coronary event, and discontinuation of AVANDAMET during this acute phase should be considered.

Patients with NYHA Class III and IV cardiac status (with or without CHF) have not been studied in controlled clinical trials. AVANDAMET is not recommended in patients with NYHA Class III and IV cardiac status.

Congestive Heart Failure During Coadministration of Rosiglitazone With Insulin:In trials in which rosiglitazone was added to insulin, rosiglitazone increased the risk of congestive heart failure. Coadministration of rosiglitazone and insulin is not recommended. [See Indications and Usage (1) and Warnings and Precautions (5.3).]

In 7 controlled, randomized, double-blind trials which had durations from 16 to 26 weeks and which were included in a meta-analysis^1 [see Warnings and Precautions (5.3)], patients with type 2 diabetes mellitus were randomized to coadministration of rosiglitazone and insulin (N = 1,018) or insulin (N = 815). In these 7 trials, rosiglitazone was added to insulin. These trials included patients with long-standing diabetes (median duration of 12 years) and a high prevalence of pre-existing medical conditions, including peripheral neuropathy, retinopathy, ischemic heart disease, vascular disease, and congestive heart failure. The total number of patients with emergent congestive heart failure was 23 (2.3%) and 8 (1.0%) in the rosiglitazone plus insulin and insulin groups, respectively.

Heart Failure in Observational Studies of Elderly Diabetic Patients Comparing Rosiglitazone to Pioglitazone: Three observational studies^2-4 in elderly diabetic patients (age 65 years and older) found that rosiglitazone statistically significantly increased the risk of hospitalized heart failure compared to use of pioglitazone. One other observational study^5 in patients with a mean age of 54 years, which also included an analysis in a subpopulation of patients >65 years of age, found no statistically significant increase in emergency department visits or hospitalization for heart failure in patients treated with rosiglitazone compared to pioglitazone in the older subgroup.

5.3 Major Adverse Cardiovascular Events

Cardiovascular adverse events have been evaluated in a meta-analysis of 52 clinical trials, in long-term, prospective, randomized, controlled trials, and in observational studies.

Meta-Analysis of Major Adverse Cardiovascular Events in a Group of 52 Clinical Trials: A meta-analysis was conducted retrospectively to assess cardiovascular adverse events reported across 52 double-blind, randomized, controlled clinical trials (mean duration 6 months).^1 These trials had been conducted to assess glucose-lowering efficacy in type 2 diabetes. Prospectively planned adjudication of cardiovascular events did not occur in most of the trials. Some trials were placebo-controlled and some used active oral antidiabetic drugs as controls. Placebo-controlled trials included monotherapy trials (monotherapy with rosiglitazone versus placebo monotherapy) and add-on trials (rosiglitazone or placebo, added to sulfonylurea, metformin, or insulin). Active control trials included monotherapy trials (monotherapy with rosiglitazone versus sulfonylurea or metformin monotherapy) and add-on trials (rosiglitazone plus sulfonylurea or rosiglitazone plus metformin, versus sulfonylurea plus metformin). A total of 16,995 patients were included (10,039 in treatment groups containing rosiglitazone, 6,956 in comparator groups), with 5,167 patient-years of exposure to rosiglitazone and 3,637 patient-years of exposure to comparator. Cardiovascular events occurred more frequently for patients who received rosiglitazone than for patients who received comparators (see Table 3).

Table 3. Occurrence of Cardiovascular Events in a Meta-Analysis of 52 Clinical Trials
Eventa | Rosiglitazone; (N=10,039); n (%) | Comparator; (N=6,956); n (%)
MACE (a composite of myocardial infarction, cardiovascular death, or stroke) | 70 (0.7) | 39 (0.6)
Myocardial Infarction | 45 (0.4) | 20 (0.3)
Cardiovascular Death | 17 (0.2) | 9 (0.1)
Stroke | 18 (0.2) | 16 (0.2)
All-cause Death | 29 (0.3) | 17 (0.2)

a Events are not exclusive: i.e., a patient with a cardiovascular death due to a myocardial infarction would be counted in 4 event categories (myocardial infarction; myocardial infarction, cardiovascular death, or stroke; cardiovascular death; all-cause death).

In this analysis, a statistically significant increased risk of myocardial infarction with rosiglitazone versus pooled comparators was observed. Analyses were performed using a composite of major adverse cardiovascular events (myocardial infarction, stroke, and cardiovascular death), referred to hereafter as MACE. Rosiglitazone had a statistically non-significant increased risk of MACE compared to the pooled comparators. A statistically significant increased risk of myocardial infarction and statistically non-significant increased risk of MACE with rosiglitazone was observed in the placebo-controlled trials. In the active-controlled trials, there was no increased risk of myocardial infarction or MACE. (See Figure 1 and Table 4.)

Figure 1. Forest Plot of Odds Ratios (95% Confidence Intervals) for MACE and Myocardial Infarction in the Meta-Analysis of 52 Clinical Trials

Table 4. Occurrence of MACE and Myocardial Infarction in a Meta-Analysis of 52 Clinical Trials by Trial Type
 |  |  | MACE |  | Myocardial Infarction
 |  | N | n (%) | OR; (95%CI) | n (%) | OR; (95%CI)
Active-; Controlled Trials | RSG | 2,119 | 16 (0.8%) | 1.05 | 10 (0.5%) | 1.00
Active-; Controlled Trials | Control | 1,918 | 14 (0.7%) | (0.48, 2.34) | 9 (0.5%) | (0.36, 2.82)
Placebo-; Controlled Trials | RSG | 8,124 | 54 (0.7%) | 1.53 | 35 (0.4%) | 2.23
Placebo-; Controlled Trials | Placebo | 5,636 | 28 (0.5%) | (0.94, 2.54) | 13 (0.2%) | (1.14, 4.64)
Overall | RSG | 10,039 | 70 (0.7%) | 1.44 | 45 (0.4%) | 1.8
Overall | Control | 6,956 | 39 (0.6%) | (0.95, 2.20) | 20 (0.3%) | (1.03, 3.25)

RSG = rosiglitazone

Of the placebo-controlled trials in the meta-analysis, 7 trials had patients randomized to rosiglitazone plus insulin or insulin. There were more patients in the rosiglitazone plus insulin group compared to the insulin group with myocardial infarctions, MACE, cardiovascular deaths, and all-cause deaths (see Table 5). The total number of patients with stroke was 5 (0.5%) and 4 (0.5%) in the rosiglitazone plus insulin and insulin groups, respectively. The use of rosiglitazone in combination with insulin may increase the risk of myocardial infarction [See Warnings and Precautions (5.1).]

Table 5. Occurrence of Cardiovascular Events for Rosiglitazone in Combination With Insulin in a Meta-Analysis of 52 Clinical Trials
Eventa | Rosiglitazone; (N=1,018); (%) | Insulin; (N = 815); (%) | OR (95% CI)
MACE (a composite of myocardial infarction, cardiovascular death, or stroke) | 1.3 | 0.6 | 2.14 (0.70, 7.83)
Myocardial infarction | 0.6 | 0.1 | 5.6 (0.67, 262.7)
Cardiovascular death | 0.4 | 0.0 | ND, (0.47, ∞)
All cause death | 0.6 | 0.2 | 2.19 (0.38, 22.61)

ND = not defined

a Events are not exclusive: i.e., a patient with a cardiovascular death due to a myocardial infarction would be counted in 4 event categories (myocardial infarction; myocardial infarction, cardiovascular death, or stroke; cardiovascular death; all-cause death).

Myocardial Infarction Events in Large, Long-Term, Prospective, Randomized, Controlled Trials of Rosiglitazone: Data from 3 large, long-term, prospective, randomized, controlled clinical trials of rosiglitazone were assessed separately from the meta-analysis.^6-8 These 3 trials included a total of 14,067 patients (treatment groups containing rosiglitazone N = 6,311; comparator groups N = 7,756), with patient-year exposure of 24,534 patient-years for rosiglitazone and 28,882 patient-years for comparator. Patient populations in the trials included patients with impaired glucose tolerance, patients with type 2 diabetes who were initiating oral agent monotherapy, and patients with type 2 diabetes who had failed monotherapy and were initiating dual oral agent therapy. Duration of follow-up exceeded 3 years in each trial.

In each of these trials, there was a statistically non-significant increase in the risk of myocardial infarction for rosiglitazone versus comparator medications.

In a long-term, randomized, placebo-controlled, 2x2 factorial trial intended to evaluate rosiglitazone, and separately ramipril (an angiotensin converting enzyme inhibitor [ACEI]), on progression to overt diabetes in 5,269 subjects with glucose intolerance, the incidence of myocardial infarction was higher in the subset of subjects who received rosiglitazone in combination with ramipril than among subjects who received ramipril alone but not in the subset of subjects who received rosiglitazone alone compared to placebo.^6 The higher incidence of myocardial infarction among subjects who received rosiglitazone in combination with ramipril was not confirmed in the two other large (total N = 8,798) long-term, randomized, active-controlled clinical trials conducted in patients with type 2 diabetes, in which 30% and 40% of patients in the two trials reported angiotensin-converting enzyme inhibitor use at baseline.^7,8

There have been no adequately designed clinical trials directly comparing rosiglitazone to pioglitazone on cardiovascular risks. However, in a long-term, randomized, placebo-controlled cardiovascular outcomes trial comparing pioglitazone to placebo in patients with type 2 diabetes mellitus and prior macrovascular disease, pioglitazone was not associated with an increased risk of myocardial infarction or total mortality.^9

The increased risk of myocardial infarction observed in the meta-analysis and large, long-term controlled clinical trials, and the increased risk of MACE observed in the meta-analysis described above, have not translated into a consistent finding of excess mortality from controlled clinical trials or observational studies. Clinical trials have not shown any difference between rosiglitazone and comparator medications in overall mortality or CV-related mortality.

Mortality in Observational Studies of Rosiglitazone Compared to Pioglitazone: Three observational studies in elderly diabetic patients (age 65 years and older) found that rosiglitazone statistically significantly increased the risk of all-cause mortality compared to use of pioglitazone.^2-4 One observational study^5 in patients with a mean age of 54 years found no difference in all-cause mortality between patients treated with rosiglitazone compared to pioglitazone and reported similar results in the subpopulation of patients >65 years of age. One additional small, prospective, observational study^10 found no statistically significant differences for CV mortality and all-cause mortality in patients treated with rosiglitazone compared to pioglitazone.

5.4 Edema

AVANDAMET should be used with caution in patients with edema. In a clinical trial in healthy volunteers who received rosiglitazone 8 mg once daily for 8 weeks, there was a statistically significant increase in median plasma volume compared to placebo. Since thiazolidinediones, including rosiglitazone, can cause fluid retention, which can exacerbate or lead to congestive heart failure, AVANDAMET should be used with caution in patients at risk for heart failure. Patients should be monitored for signs and symptoms of heart failure [see Boxed Warning, Warnings and Precautions (5.2), and Patient Counseling Information (17.1)].

In controlled clinical trials of patients with type 2 diabetes, mild to moderate edema was reported in patients treated with rosiglitazone, and may be dose-related. Patients with ongoing edema were more likely to have adverse events associated with edema if started on combination therapy with insulin and rosiglitazone [see Adverse Reactions (6.1)]. The use of AVANDAMET in combination with insulin is not recommended. [See Warnings and Precautions (5.2, 5.3).]

5.5 Weight Gain

Dose-related weight gain was seen with rosiglitazone alone and rosiglitazone together with other hypoglycemic agents (see Table 6). No overall change in median weight was observed with AVANDAMET in drug-naïve patients. The mechanism of weight gain with rosiglitazone is unclear but probably involves a combination of fluid retention and fat accumulation.

Table 6. Weight Changes (kg) From Baseline at Endpoint During Clinical Trials [Median (25th, 75th, Percentile)]
Monotherapy
Duration | Control Group |  | Rosiglitazone 4 mg | Rosiglitazone 8 mg
26 weeks | Placebo | -0.9 (-2.8, 0.9); N = 210 | 1.0 (0.9, 3.6); N = 436 | 3.1 (1.1, 5.8); N = 439
52 weeks | Sulfonylurea | 2.0 (0, 4.0); N = 173 | 2.0 (-0.6, 4.0); N = 150 | 2.6 (0, 5.3); N = 157
Combination Therapy
 |  |  |  | Rosiglitazone + Control Therapy
Duration | Control Group |  | Rosiglitazone 4 mg | Rosiglitazone 8 mg
24-26 weeks | Sulfonylurea | 0 (-1.0, 1.3); N = 1,155 | 2.2 (0.5, 4.0); N = 613 | 3.5 (1.4, 5.9); N = 841
26 weeks | Metformin | -1.4 (-3.2, 0.2); N = 175 | 0.8 (-1.0, 2.6); N = 100 | 2.1 (0, 4.3); N = 184
26 weeks | Insulin | 0.9 (-0.5, 2.7); N = 162 | 4.1 (1.4, 6.3); N = 164 | 5.4 (3.4, 7.3); N = 150
AVANDAMET + Insulin
Duration | Control Group |  |  | AVANDAMET + Insulin
24 weeks | Insulin | 2.6 kg (0.3, 4.8); N = 145 |  | 3.3 kg (1.5, 6.0); N = 147

In a 4- to 6-year, monotherapy, comparative trial (ADOPT) in patients recently diagnosed with type 2 diabetes not previously treated with antidiabetic medication, the median weight change (25th, 75th percentiles) from baseline at 4 years was 3.5 kg (0.0, 8.1) for rosiglitazone, 2.0 kg (-1.0, 4.8) for glyburide, and -2.4 kg (-5.4, 0.5) for metformin.

In postmarketing experience with rosiglitazone alone or in combination with other hypoglycemic agents, there have been rare reports of unusually rapid increases in weight and increases in excess of that generally observed in clinical trials. Patients who experience such increases should be assessed for fluid accumulation and volume-related events such as excessive edema and congestive heart failure [see Boxed Warning].

5.6 Hepatic Effects

Metformin: Since impaired hepatic function has been associated with some cases of lactic acidosis, AVANDAMET should generally be avoided in patients with clinical or laboratory evidence of hepatic disease.

Rosiglitazone: Liver enzymes should be measured prior to the initiation of therapy with AVANDAMET in all patients and periodically thereafter per the clinical judgment of the healthcare professional. Therapy with AVANDAMET should not be initiated in patients with increased baseline liver enzyme levels (ALT >2.5X upper limit of normal). Patients with mildly elevated liver enzymes (ALT levels ≤2.5X upper limit of normal) at baseline or during therapy with AVANDAMET should be evaluated to determine the cause of the liver enzyme elevation. Initiation of, or continuation of, therapy with AVANDAMET in patients with mild liver enzyme elevations should proceed with caution and include close clinical follow-up, including more frequent liver enzyme monitoring, to determine if the liver enzyme elevations resolve or worsen. If at any time ALT levels increase to >3X the upper limit of normal in patients on therapy with AVANDAMET, liver enzyme levels should be rechecked as soon as possible. If ALT levels remain >3X the upper limit of normal, therapy with AVANDAMET should be discontinued.

If any patient develops symptoms suggesting hepatic dysfunction, which may include unexplained nausea, vomiting, abdominal pain, fatigue, anorexia, and/or dark urine, liver enzymes should be checked. The decision whether to continue the patient on therapy with AVANDAMET should be guided by clinical judgment pending laboratory evaluations. If jaundice is observed, drug therapy should be discontinued.

In addition, if the presence of hepatic disease or hepatic dysfunction of sufficient magnitude to predispose to lactic acidosis is confirmed, therapy with AVANDAMET should be discontinued.

5.7 Macular Edema

Macular edema has been reported in postmarketing experience in some diabetic patients who were taking rosiglitazone or another thiazolidinedione. Some patients presented with blurred vision or decreased visual acuity, but some patients appear to have been diagnosed on routine ophthalmologic examination. Most patients had peripheral edema at the time macular edema was diagnosed. Some patients had improvement in their macular edema after discontinuation of their thiazolidinedione. Patients with diabetes should have regular eye exams by an ophthalmologist, per the Standards of Care of the American Diabetes Association. Additionally, any diabetic who reports any kind of visual symptom should be promptly referred to an ophthalmologist, regardless of the patient’s underlying medications or other physical findings. [See Adverse Reactions (6.3).]

5.8 Fractures

In a 4- to 6-year comparative trial (ADOPT) of glycemic control with monotherapy in drug-naïve patients recently diagnosed with type 2 diabetes mellitus, an increased incidence of bone fracture was noted in female patients taking rosiglitazone. Over the 4- to 6-year period, the incidence of bone fracture in females was 9.3% (60/645) for rosiglitazone versus 3.5% (21/605) for glyburide and 5.1% (30/590) for metformin. This increased incidence was noted after the first year of treatment and persisted during the course of the trial. The majority of the fractures in the women who received rosiglitazone occurred in the upper arm, hand, and foot. These sites of fracture are different from those usually associated with postmenopausal osteoporosis (e.g., hip or spine). Other trials suggest that this risk may also apply to men, although the risk of fracture among women appears higher than that among men. The risk of fracture should be considered in the care of patients treated with rosiglitazone, and attention given to assessing and maintaining bone health according to current standards of care.

5.9 Hematologic Effects

Decreases in mean hemoglobin and hematocrit occurred in a dose-related fashion in adult patients treated with rosiglitazone [see Adverse Reactions (6.2)]. The observed changes may be related to the increased plasma volume observed with treatment with rosiglitazone and may be dose-related. The decrease in hemoglobin was seen more frequently in combination rosiglitazone and metformin therapy than in rosiglitazone therapy alone. Vitamin B12 deficiency may contribute to the observed reductions in hemoglobin [see Warnings and Precautions (5.10)]. Initial and periodic monitoring of hematologic parameters (e.g., hemoglobin/hematocrit and red blood cell indices) should be performed, at least on an annual basis.

5.10 Vitamin B12 Levels

In controlled clinical trials of metformin of 29 weeks’ duration, a decrease to subnormal levels of previously normal serum vitamin B12 levels, without clinical manifestations, was observed in approximately 7% of patients. Such decrease, possibly due to interference with B12 absorption from the B12-intrinsic factor complex, is, however, very rarely associated with anemia and appears to be rapidly reversible with discontinuation of metformin or vitamin B12 supplementation. Certain individuals (those with inadequate vitamin B12 or calcium intake or absorption) appear to be predisposed to developing subnormal vitamin B12 levels. In these patients, routine serum vitamin B12 measurements at 2- to 3-year intervals may be useful. Vitamin B12 deficiency should be excluded if megaloblastic anemia is suspected. [See Warnings and Precautions (5.9).]

5.11 Diabetes and Blood Glucose Control

Periodic fasting blood glucose and HbA1c measurements should be performed to monitor therapeutic response.

When a patient stabilized on any diabetic regimen is exposed to stress such as fever, trauma, infection, or surgery, a temporary loss of glycemic control may occur. At such times, it may be necessary to withhold AVANDAMET and temporarily administer insulin. AVANDAMET may be reinstituted after the acute episode is resolved.

Hypoglycemia does not occur in patients receiving metformin alone under usual circumstances of use but could occur when caloric intake is deficient, when strenuous exercise is not compensated by caloric supplementation, or during concomitant use with hypoglycemic agents (such as sulfonylureas or insulin) or ethanol. Elderly, debilitated or malnourished patients, and those with adrenal or pituitary insufficiency or alcohol intoxication are particularly susceptible to hypoglycemic effects. Hypoglycemia may be difficult to recognize in the elderly and in people who are taking β-adrenergic blocking drugs.

Patients receiving rosiglitazone in combination with other hypoglycemic agents may be at risk for hypoglycemia, and a reduction in the dose of the concomitant agent may be necessary.

5.12 Ovulation

Therapy with rosiglitazone, like other thiazolidinediones, may result in ovulation in some premenopausal anovulatory women. As a result, these patients may be at an increased risk for pregnancy while taking AVANDAMET [see Use in Specific Populations (8.1)]. Thus, adequate contraception in premenopausal women should be recommended. This possible effect has not been specifically investigated in clinical trials; therefore, the frequency of this occurrence is not known.

Although hormonal imbalance has been seen in preclinical studies [see Nonclinical Toxicology (13.1)], the clinical significance of this finding is not known. If unexpected menstrual dysfunction occurs, the benefits of continued therapy with AVANDAMET should be reviewed.

6 ADVERSE REACTIONS

6.1 Clinical Trial Experience

Because clinical trials are conducted under widely varying conditions, adverse reaction rates observed in the clinical trials of a drug cannot be directly compared to rates in the clinical trials of another drug and may not reflect the rates observed in practice.

The incidence and types of adverse events reported in controlled, 26-week clinical trials of rosiglitazone administered in combination with metformin 2,500 mg/day in comparison to adverse reactions reported in association with rosiglitazone and metformin monotherapies are shown in Table 7. Overall, the types of adverse reactions without regard to causality reported when rosiglitazone was used in combination with metformin were similar to those reported during monotherapy with rosiglitazone.

Table 7. Adverse Events (≥5% for Rosiglitazone Plus Metformin) Reported by Patients in 26-week Double-blind Clinical Trials of Rosiglitazone Added to Metformin Therapy
 | Rosiglitazone + Metformin | Rosiglitazone | Placebo | Metformin
 | N = 338 | N = 2,526 | N = 601 | N = 225
Preferred term | % | % | % | %
Upper respiratory tract infection | 16.0 | 9.9 | 8.7 | 8.9
Diarrhea | 12.7 | 2.3 | 3.3 | 15.6
Injury | 8.0 | 7.6 | 4.3 | 7.6
Anemia | 7.1 | 1.9 | 0.7 | 2.2
Headache | 6.5 | 5.9 | 5.0 | 8.9
Sinusitis | 6.2 | 3.2 | 4.5 | 5.3
Fatigue | 5.9 | 3.6 | 5.0 | 4.0
Back pain | 5.0 | 4.0 | 3.8 | 4.0
Viral infection | 5.0 | 3.2 | 4.0 | 3.6
Arthralgia | 5.0 | 3.0 | 4.0 | 2.2

Reports of hypoglycemia in patients treated with rosiglitazone added to maximum metformin therapy in double-blind trials were more frequent (3.0%) than in patients treated with rosiglitazone (0.6%) or metformin monotherapies (1.3%) or placebo (0.2%). Overall, anemia and edema were generally mild to moderate in severity and usually did not require discontinuation of treatment with rosiglitazone.

Edema was reported in 4.8% of patients receiving rosiglitazone compared to 1.3% on placebo, and 2.2% on metformin monotherapy and 4.4% on rosiglitazone in combination with maximum doses of metformin.

Reports of anemia (7.1%) were greater in patients treated with rosiglitazone added to metformin compared to monotherapy with rosiglitazone. Lower pre-treatment hemoglobin/hematocrit levels in patients enrolled in the metformin and rosiglitazone combination therapy clinical trials may have contributed to the higher reporting rate of anemia in these trials [see Adverse Reactions (6.2)].

Combination with Insulin: The incidence of hypoglycemia (confirmed by fingerstick blood glucose concentration ≤50 mg/dL) was 14% for patients on AVANDAMET plus insulin compared to 10% for patients on insulin monotherapy.

The incidence of edema was 7% when insulin was added to AVANDAMET compared to 3% with insulin monotherapy. This trial excluded patients with pre-existing heart failure or new or worsening edema on AVANDAMET therapy. However, in 26-week double-blind, fixed-dose trials of rosiglitazone added to insulin, edema was reported with higher frequency (rosiglitazone in combination with insulin, 14.7%; insulin, 5.4%) [see Warnings and Precautions (5.2)].

In trials in which rosiglitazone was added to insulin, rosiglitazone increased the risk of congestive heart failure. The use of rosiglitazone in combination with insulin may increase the risk of myocardial infarction [see Warnings and Precautions (5.2, 5.3)].

In a trial in which insulin was added to AVANDAMET, no myocardial ischemia was observed in the insulin group (N = 158), and no congestive heart failure was reported in either group. There was one myocardial ischemic event and one sudden death in the group receiving AVANDAMET plus insulin (N = 161). [See Warnings and Precautions (5.2).]

The incidence of anemia was 2% for AVANDAMET in combination with insulin compared to 1% for insulin monotherapy.

A long-term, 4- to 6-year trial (ADOPT) compared the use of rosiglitazone (n = 1,456), glyburide (n = 1,441), and metformin (n = 1,454) as monotherapy in patients recently diagnosed with type 2 diabetes who were not previously treated with antidiabetic medication. Table 8 presents adverse reactions without regard to causality; rates are expressed per 100 patient-years (PY) exposure to account for the differences in exposure to trial medication across the 3 treatment groups.

In ADOPT, fractures were reported in a greater number of women treated with rosiglitazone (9.3%, 2.7/100 patient-years) compared to glyburide (3.5%, 1.3/100 patient-years) or metformin (5.1%, 1.5/100 patient-years). The majority of the fractures in the women who received rosiglitazone were reported in the upper arm, hand, and foot. [See Warnings and Precautions (5.8).] The observed incidence of fractures for male patients was similar among the 3 treatment groups.

Table 8. On-Therapy Adverse Events (≥5 Events/100 Patient-Years [PY]) in Any Treatment Group Reported in a 4- to 6-Year Clinical Trial of Rosiglitazone as Monotherapy (ADOPT)
 | Rosiglitazone | Glyburide | Metformin
 | N = 1,456 | N = 1,441 | N = 1,454
 | PY = 4,954 | PY = 4,244 | PY = 4,906
Nasopharyngitis | 6.3 | 6.9 | 6.6
Back pain | 5.1 | 4.9 | 5.3
Arthralgia | 5.0 | 4.8 | 4.2
Hypertension | 4.4 | 6.0 | 6.1
Upper respiratory tract infection | 4.3 | 5.0 | 4.7
Hypoglycemia | 2.9 | 13.0 | 3.4
Diarrhea | 2.5 | 3.2 | 6.8

6.2 Laboratory Abnormalities

Hematologic: Decreases in mean hemoglobin and hematocrit occurred in a dose-related fashion in adult patients treated with rosiglitazone (mean decreases in individual trials as much as 1.0 gram/dL hemoglobin and as much as 3.3% hematocrit). The changes occurred primarily during the first 3 months following initiation of rosiglitazone therapy or following an increase in rosiglitazone dose. The time course and magnitude of decreases were similar in patients treated with a combination of rosiglitazone and other hypoglycemic agents or monotherapy with rosiglitazone. Pre-treatment levels of hemoglobin and hematocrit were lower in patients in metformin combination trials and may have contributed to the higher reporting rate of anemia. In a single trial in pediatric patients, decreases in hemoglobin and hematocrit (mean decreases of 0.29 g/dL and 0.95%, respectively) were reported with rosiglitazone. White blood cell counts also decreased slightly in adult patients treated with rosiglitazone. Decreases in hematologic parameters may be related to increased plasma volume observed with rosiglitazone treatment.

In controlled clinical trials of metformin of 29 weeks’ duration, a decrease to subnormal levels of previously normal serum vitamin B12 levels, without clinical manifestations, was observed in approximately 7% of patients. Such a decrease, possibly due to interference with B12 absorption from the B12-intrinsic factor complex, is, however, very rarely associated with anemia and appears to be rapidly reversible with discontinuation of metformin or vitamin B12 supplementation.

Lipids: Changes in serum lipids have been observed following treatment with rosiglitazone in adults [see Clinical Pharmacology (12.2)].

Serum Transaminase Levels: In pre-approval clinical trials in 4,598 patients treated with rosiglitazone encompassing approximately 3,600 patient years of exposure, and in a long-term 4- to 6-year trial in 1,456 patients treated with rosiglitazone (4,954 patient-years exposure), there was no evidence of drug-induced hepatotoxicity.

In pre-approval controlled trials, 0.2% of patients treated with rosiglitazone had reversible elevations in ALT >3X the upper limit of normal compared to 0.2% on placebo and 0.5% on active comparators. The ALT elevations in patients treated with rosiglitazone were reversible. Hyperbilirubinemia was found in 0.3% of patients treated with rosiglitazone compared with 0.9% treated with placebo and 1% in patients treated with active comparators. In pre-approval clinical trials, there were no cases of idiosyncratic drug reactions leading to hepatic failure. [See Warnings and Precautions (5.6).]

In the 4- to 6-year ADOPT trial, patients treated with rosiglitazone (4,954 patient-years exposure), glyburide (4,244 patient-years exposure) or metformin (4,906 patient-years exposure) as monotherapy, had the same rate of ALT increase to >3X upper limit of normal (0.3 per 100 patient-years exposure).

6.3 Postmarketing Experience

In addition to adverse reactions reported from clinical trials, the events described below have been identified during post-approval use of AVANDAMET or its individual components. Because these events are reported voluntarily from a population of unknown size, it is not possible to reliably estimate their frequency or to always establish a causal relationship to drug exposure.

In patients receiving thiazolidinedione therapy, serious adverse events with or without a fatal outcome, potentially related to volume expansion (e.g., congestive heart failure, pulmonary edema, and pleural effusions) have been reported [see Boxed Warning and Warnings and Precautions (5.2)].

There are postmarketing reports with rosiglitazone of hepatitis, hepatic enzyme elevations to 3 or more times the upper limit of normal, and hepatic failure with and without fatal outcome, although causality has not been established.

There are postmarketing reports with rosiglitazone of rash, pruritus, urticaria, angioedema, anaphylactic reaction, Stevens-Johnson syndrome, and new onset or worsening diabetic macular edema with decreased visual acuity [see Warnings and Precautions (5.7)].

(See also GLUCOPHAGE® prescribing information.)

7 DRUG INTERACTIONS

7.1 Drugs Metabolized by Cytochrome P450

An inhibitor of CYP2C8 (e.g., gemfibrozil) may increase the AUC of rosiglitazone and an inducer of CYP2C8 (e.g., rifampin) may decrease the AUC of rosiglitazone. Therefore, if an inhibitor or an inducer of CYP2C8 is started or stopped during treatment with rosiglitazone, changes in diabetes treatment may be needed based upon clinical response. [See Clinical Pharmacology (12.4).]

7.2 Cationic Drugs

Although drug interactions for metformin with cationic drugs (e.g., amiloride, digoxin, morphine, procainamide, quinidine, quinine, ranitidine, triamterene, trimethoprim, and vancomycin) remain theoretical (except for cimetidine), careful patient monitoring and dose adjustment of AVANDAMET and/or the interfering drug is recommended in patients who are taking cationic medications that are excreted via the proximal renal tubular secretory system. [See Warnings and Precautions (5.1) and Clinical Pharmacology (12.4).]

7.3 Drugs That Produce Hyperglycemia

When drugs that produce hyperglycemia which may lead to loss of glycemic control are administered to a patient receiving AVANDAMET, the patient should be closely observed to maintain adequate glycemic control. [See Clinical Pharmacology (12.4).]

8 USE IN SPECIFIC POPULATIONS

8.1 Pregnancy

Pregnancy Category C.

All pregnancies have a background risk of birth defects, loss, or other adverse outcome regardless of drug exposure. This background risk is increased in pregnancies complicated by hyperglycemia and may be decreased with good metabolic control. It is essential for patients with diabetes or history of gestational diabetes to maintain good metabolic control before conception and throughout pregnancy. Careful monitoring of glucose control is essential in such patients. Most experts recommend that insulin monotherapy be used during pregnancy to maintain blood glucose levels as close to normal as possible. AVANDAMET should not be used during pregnancy.

Human Data: There are no adequate and well-controlled trials with AVANDAMET or its individual components in pregnant women. Rosiglitazone has been reported to cross the human placenta and be detectable in fetal tissue. The clinical significance of these findings is unknown.

Animal Studies: No animal studies have been conducted with AVANDAMET. The following data are based on findings in studies performed with rosiglitazone or metformin individually.

Rosiglitazone: There was no effect on implantation or the embryo with rosiglitazone treatment during early pregnancy in rats, but treatment during mid-late gestation was associated with fetal death and growth retardation in both rats and rabbits. Teratogenicity was not observed at doses up to 3 mg/kg in rats and 100 mg/kg in rabbits (approximately 20 and 75 times human AUC at the maximum recommended human daily dose of the rosiglitazone component of AVANDAMET, respectively). Rosiglitazone caused placental pathology in rats (3 mg/kg/day). Treatment of rats during gestation through lactation reduced litter size, neonatal viability, and postnatal growth, with growth retardation reversible after puberty. For effects on the placenta, embryo/fetus, and offspring, the no-effect dose was 0.2 mg/kg/day in rats and 15 mg/kg/day in rabbits. These no-effect levels are approximately 4 times human AUC at the maximum recommended human daily dose of the rosiglitazone component of AVANDAMET. Rosiglitazone reduced the number of uterine implantations and live offspring when juvenile female rats were treated at 40 mg/kg/day from 27 days of age through to sexual maturity (approximately 68 times human AUC at the maximum recommended daily dose). The no-effect level was 2 mg/kg/day (approximately 4 times human AUC at the maximum recommended daily dose). There was no effect on pre- or post-natal survival or growth.

Metformin: Metformin was not teratogenic in rats and rabbits at doses up to 600 mg/kg/day. This represents an exposure of about 2 and 6 times the maximum recommended human daily dose of 2,000 mg based on body surface area comparisons for rats and rabbits, respectively. Determination of fetal concentrations demonstrated a partial placental barrier to metformin.

8.2 Labor and Delivery

The effect of AVANDAMET or its components on labor and delivery in humans is unknown.

8.3 Nursing Mothers

No studies have been conducted with AVANDAMET. In studies performed with the individual components, both rosiglitazone-related material and metformin were detectable in milk from lactating rats. It is not known whether rosiglitazone or metformin is excreted in human milk. Because many drugs are excreted in human milk, AVANDAMET should not be administered to a nursing woman.

8.4 Pediatric Use

Safety and effectiveness of AVANDAMET in pediatric patients have not been established. AVANDAMET and rosiglitazone are not indicated for use in pediatric patients.

8.5 Geriatric Use

Metformin is known to be substantially excreted by the kidney and because the risk of serious adverse reactions to the drug is greater in patients with impaired renal function, AVANDAMET should only be used in patients with normal renal function [see Contraindications (4), Warnings and Precautions (5.1), and Clinical Pharmacology (12.3)]. Because reduced renal function is associated with increasing age, AVANDAMET should be used with caution in elderly patients. Care should be taken in dose selection and should be based on careful and regular monitoring of renal function. Generally, elderly patients should not be titrated to the maximum dose of AVANDAMET [see Dosage and Administration (2.4) and Warnings and Precautions (5.1)].

10 OVERDOSAGE

Rosiglitazone: Limited data are available with regard to overdosage in humans. In clinical trials in volunteers, rosiglitazone has been administered at single oral doses of up to 20 mg and was well tolerated. In the event of an overdose, appropriate supportive treatment should be initiated as dictated by the patient’s clinical status.

Metformin: Hypoglycemia has not been seen with ingestion of up to 85 grams of metformin, although lactic acidosis has occurred in such circumstances [see Warnings and Precautions (5.1)]. Metformin is dialyzable with a clearance of up to 170 mL/min under good hemodynamic conditions. Therefore, hemodialysis may be useful for removal of accumulated metformin from patients in whom metformin overdosage is suspected.

11 DESCRIPTION

AVANDAMET contains 2 oral antidiabetic drugs: rosiglitazone maleate and metformin hydrochloride.

Rosiglitazone maleate is an oral antidiabetic agent, which acts primarily by increasing insulin sensitivity. Rosiglitazone improves glycemic control while reducing circulating insulin levels. Rosiglitazone maleate is not chemically or functionally related to the sulfonylureas, the biguanides, or the alpha-glucosidase inhibitors. Chemically, rosiglitazone maleate is (±)-5-[[4-[2-(methyl-2-pyridinylamino)ethoxy]phenyl]methyl]-2,4-thiazolidinedione, (Z)-2-butenedioate (1:1) with a molecular weight of 473.52 (357.44 free base). The molecule has a single chiral center and is present as a racemate. Due to rapid interconversion, the enantiomers are functionally indistinguishable. The molecular formula is C18H19N3O3S•C4H4O4. Rosiglitazone maleate is a white to off-white solid with a melting point range of 122° to 123°C. The pKa values of rosiglitazone maleate are 6.8 and 6.1. It is readily soluble in ethanol and a buffered aqueous solution with pH of 2.3; solubility decreases with increasing pH in the physiological range. The structural formula of rosiglitazone maleate is:

Metformin hydrochloride (N,N-dimethylimidodicarbonimidic diamide hydrochloride) is not chemically or pharmacologically related to any other classes of oral antidiabetic agents. Metformin hydrochloride is a white to off-white crystalline compound with a molecular formula of C4H11N5•HCl and a molecular weight of 165.63. Metformin hydrochloride is freely soluble in water and is practically insoluble in acetone, ether, and chloroform. The pKa of metformin is 12.4. The pH of a 1% aqueous solution of metformin hydrochloride is 6.68. The structural formula of metformin hydrochloride is:

AVANDAMET is available for oral administration as film-coated tablets containing rosiglitazone maleate and metformin hydrochloride equivalent to: 2 mg rosiglitazone with 500 mg metformin hydrochloride (2 mg/500 mg), 4 mg rosiglitazone with 500 mg metformin hydrochloride (4 mg/500 mg), 2 mg rosiglitazone with 1,000 mg metformin hydrochloride (2 mg/1,000 mg), and 4 mg rosiglitazone with 1,000 mg metformin hydrochloride (4 mg/1,000 mg). Inactive ingredients are: Hypromellose 2910, lactose monohydrate, magnesium stearate, microcrystalline cellulose, polyethylene glycol 400, povidone 29-32, sodium starch glycolate, titanium dioxide, and 1 or more of the following: Red and yellow iron oxides.

12 CLINICAL PHARMACOLOGY

12.1 Mechanism of Action

AVANDAMET: AVANDAMET combines 2 antidiabetic agents with different mechanisms of action to improve glycemic control in patients with type 2 diabetes: Rosiglitazone, a member of the thiazolidinedione class, and metformin, a member of the biguanide class. Thiazolidinediones are insulin sensitizing agents that act primarily by enhancing peripheral glucose utilization, whereas biguanides act primarily by decreasing endogenous hepatic glucose production.

Rosiglitazone: Rosiglitazone improves glycemic control by improving insulin sensitivity. Rosiglitazone is a highly selective and potent agonist for the peroxisome proliferator–activated receptor-gamma (PPARγ). In humans, PPAR receptors are found in key target tissues for insulin action such as adipose tissue, skeletal muscle, and liver. Activation of PPARγ nuclear receptors regulates the transcription of insulin-responsive genes involved in the control of glucose production, transport, and utilization. In addition, PPARγ-responsive genes also participate in the regulation of fatty acid metabolism.

Insulin resistance is a common feature characterizing the pathogenesis of type 2 diabetes. The antidiabetic activity of rosiglitazone has been demonstrated in animal models of type 2 diabetes in which hyperglycemia and/or impaired glucose tolerance is a consequence of insulin resistance in target tissues. Rosiglitazone reduces blood glucose concentrations and reduces hyperinsulinemia in the ob/ob obese mouse, db/db diabetic mouse, and fa/fa fatty Zucker rat.

In animal models, the antidiabetic activity of rosiglitazone was shown to be mediated by increased sensitivity to insulin's action in the liver, muscle, and adipose tissue. Pharmacologic studies in animal models indicate that rosiglitazone improves sensitivity to insulin in muscle and adipose tissue and inhibits hepatic gluconeogenesis. The expression of the insulin-regulated glucose transporter GLUT-4 was increased in adipose tissue. Rosiglitazone did not induce hypoglycemia in animal models of type 2 diabetes and/or impaired glucose tolerance.

Metformin: Metformin is an antidiabetic agent, which improves glucose tolerance in patients with type 2 diabetes, lowering both basal and postprandial plasma glucose. Its pharmacologic mechanisms of action are different from other classes of oral antidiabetic agents. Metformin decreases hepatic glucose production, decreases intestinal absorption of glucose, and increases peripheral glucose uptake and utilization. Unlike sulfonylureas, metformin does not produce hypoglycemia in either patients with type 2 diabetes or normal subjects except in special circumstances [see Warnings and Precautions (5.11)] and does not cause hyperinsulinemia. With metformin therapy, insulin secretion remains unchanged while fasting insulin levels and day-long plasma insulin response may actually decrease.

12.2 Pharmacodynamics

In all 26-week controlled trials, across the recommended dose range, rosiglitazone as monotherapy was associated with increases in total cholesterol, LDL-cholesterol and HDL-cholesterol and decreases in free fatty acids.

The lipid profiles of AVANDAMET as well as rosiglitazone and metformin monotherapies in patients who have inadequate glycemic control on diet and exercise are shown in Table 9.

Table 9. Summary of Meana Lipid Changes in a 32-Week Trial of AVANDAMET in Patients with Type 2 Diabetes Mellitus Who Have Inadequate Glycemic Control on Diet and Exercise
 | AVANDAMET; Nb = 132 | Rosiglitazone; Nb = 128 | Metformin; Nb = 117
Total Cholesterol (mg/dL)
Baseline (mean) | 200.4 | 198.4 | 201.6
% Change from baseline (mean) | -2.2% | 5.3% | -9.0%
LDL (mg/dL)
Baseline (mean) | 113.8 | 114.6 | 116.0
% Change from baseline (mean) | -0.2% | 4.5% | -10.7%
HDL (mg/dL)
Baseline (mean) | 42.6 | 42.8 | 42.9
% Change from baseline (mean) | 5.8% | 3.1% | 0.0%
Triglycerides (mg/dL)
Baseline (mean) | 180.3 | 166.6 | 175.7
% Change from baseline (mean) | -18.7% | -4.8% | -15.4%

aData presented as geometric means throughout table.

bN = number of subjects with a baseline and end of treatment value.

The pattern of LDL, HDL, and total cholesterol changes following therapy with rosiglitazone added to metformin was generally similar to those seen with rosiglitazone monotherapy, and a small decrease in mean triglycerides was observed with the combination therapy.

12.3 Pharmacokinetics

Absorption: AVANDAMET: In a bioequivalence and dose proportionality trial of AVANDAMET 4 mg/500 mg, both the rosiglitazone component and the metformin component were bioequivalent to coadministered 4 mg rosiglitazone tablet and 500 mg metformin tablet under fasted conditions (see Table 10). In this trial, dose proportionality of rosiglitazone in the combination formulations of 1 mg/500 mg and 4 mg/500 mg was demonstrated.

Table 10. Mean (SD) Pharmacokinetic Parameters for Rosiglitazone and Metformin
 |  | Pharmacokinetic Parameter
Regimen | N | AUC0-inf (ng.h/mL) | Cmax (ng/mL) | Tmax a; (h) | T½; (h)
Rosiglitazone
A | 25 | 1,442; (324) | 242; (70) | 0.95; (0.48-2.47) | 4.26; (1.18)
B | 25 | 1,398; (340) | 254; (69) | 0.57; (0.43-2.58) | 3.95; (0.81)
C | 24 | 349; (91) | 63.0; (15.0) | 0.57; (0.47-1.45) | 3.87; (0.88)
Metformin
A | 25 | 7,116; (2,096) | 1,106; (329) | 2.97; (1.02-4.02) | 3.46; (0.96)
B | 25 | 7,413; (1,838) | 1,135; (253) | 2.50; (1.03-3.98) | 3.36; (0.54)
C | 24 | 6,945; (2,045) | 1,080; (327) | 2.97; (1.00-5.98) | 3.35; (0.59)

aMedian and range presented for Tmax.

Regimen A = 4 mg/500 mg AVANDAMET; Regimen B = 4 mg rosiglitazone tablet + 500 mg metformin tablet; Regimen C = 1 mg/500 mg AVANDAMET

Administration of AVANDAMET 4 mg/500 mg with food resulted in no change in overall exposure (AUC) for either rosiglitazone or metformin. However, there were decreases in Cmax of both components (22% for rosiglitazone and 15% for metformin, respectively) and a delay in Tmax of both components (1.5 hours for rosiglitazone and 0.5 hours for metformin, respectively). These changes are not likely to be clinically significant. The pharmacokinetics of both the rosiglitazone component and the metformin component of AVANDAMET when taken with food were similar to the pharmacokinetics of rosiglitazone and metformin when administered concomitantly as separate tablets with food.

Absorption: Rosiglitazone: The absolute bioavailability of rosiglitazone is 99%. Peak plasma concentrations are observed about 1 hour after dosing. Maximum plasma concentration (Cmax) and the area under the curve (AUC) of rosiglitazone increase in a dose-proportional manner over the therapeutic dose range.

Absorption: Metformin: The absolute bioavailability of a 500 mg metformin tablet given under fasting conditions is approximately 50% to 60%. Trials using single oral doses of metformin tablets of 500 mg to 1,500 mg, and 850 mg to 2,550 mg, indicate that there is a lack of dose proportionality with increasing doses, which is due to decreased absorption rather than an alteration in elimination.

Distribution: Rosiglitazone: The mean (CV%) oral volume of distribution (Vss/F) of rosiglitazone is approximately 17.6 (30%) liters, based on a population pharmacokinetic analysis. Rosiglitazone is approximately 99.8% bound to plasma proteins, primarily albumin.

Distribution: Metformin: The apparent volume of distribution (V/F) of metformin following single oral doses of 850 mg metformin averaged 654 ± 358 L. Metformin is negligibly bound to plasma proteins. Metformin partitions into erythrocytes, most likely as a function of time. At usual clinical doses and dosing schedules of metformin, steady-state plasma concentrations of metformin are reached within 24 to 48 hours and are generally <1 mcg/mL. During controlled clinical trials, maximum metformin plasma levels did not exceed 5 mcg/mL, even at maximum doses.

Metabolism and Excretion: Rosiglitazone: Rosiglitazone is extensively metabolized with no unchanged drug excreted in the urine. The major routes of metabolism were N-demethylation and hydroxylation, followed by conjugation with sulfate and glucuronic acid. All the circulating metabolites are considerably less potent than parent and, therefore, are not expected to contribute to the insulin-sensitizing activity of rosiglitazone. In vitro data demonstrate that rosiglitazone is predominantly metabolized by Cytochrome P450 (CYP) isoenzyme 2C8, with CYP2C9 contributing as a minor pathway. Following oral or intravenous administration of [^14C]rosiglitazone maleate, approximately 64% and 23% of the dose was eliminated in the urine and in the feces, respectively. The plasma half-life of [^14C]related material ranged from 103 to 158 hours. The elimination half-life is 3 to 4 hours and is independent of dose.

Metabolism and Excretion: Metformin: Intravenous single-dose trials in normal subjects demonstrate that metformin is excreted unchanged in the urine and does not undergo hepatic metabolism (no metabolites have been identified in humans) nor biliary excretion. Renal clearance is approximately 3.5 times greater than creatinine clearance which indicates that tubular secretion is the major route of metformin elimination. Following oral administration, approximately 90% of the absorbed drug is eliminated via the renal route within the first 24 hours, with a plasma elimination half-life of approximately 6.2 hours. In blood, the elimination half-life is approximately 17.6 hours, suggesting that the erythrocyte mass may be a compartment of distribution.

Special Populations: Renal Impairment: In subjects with decreased renal function (based on measured creatinine clearance), the plasma and blood half-life of metformin is prolonged and the renal clearance is decreased in proportion to the decrease in creatinine clearance [see Warnings and Precautions (5.1) and GLUCOPHAGE prescribing information]. Since metformin is contraindicated in patients with renal impairment, administration of AVANDAMET is contraindicated in these patients.

Hepatic Impairment: Unbound oral clearance of rosiglitazone was significantly lower in patients with moderate to severe liver disease (Child-Pugh Class B/C) compared to healthy subjects. As a result, unbound Cmax and AUC0-inf were increased 2- and 3-fold, respectively. Elimination half-life for rosiglitazone was about 2 hours longer in patients with liver disease, compared to healthy subjects.

Therapy with AVANDAMET should not be initiated if the patient exhibits clinical evidence of active liver disease or increased serum transaminase levels (ALT >2.5X upper limit of normal) at baseline [see Warnings and Precautions (5.6)].

No pharmacokinetic trials of metformin have been conducted in subjects with hepatic insufficiency.

Geriatric: Results of the population pharmacokinetics analysis (N = 716 <65 years; N = 331 ≥65 years) showed that age does not significantly affect the pharmacokinetics of rosiglitazone. However, limited data from controlled pharmacokinetic trials of metformin in healthy elderly subjects suggest that total plasma clearance of metformin is decreased, the half-life is prolonged, and Cmax is increased, compared to healthy young subjects. From these data, it appears that the change in metformin pharmacokinetics with aging is primarily accounted for by a change in renal function [see Use in Specific Populations (8.5) and GLUCOPHAGE prescribing information]. Metformin treatment and therefore treatment with AVANDAMET should not be initiated in patients ≥80 years of age unless measurement of creatinine clearance demonstrates that renal function is not reduced [see Dosage and Administration (2) and Warnings and Precautions (5.1)].

Gender: Results of the population pharmacokinetics analysis showed that the mean oral clearance of rosiglitazone in female patients (N = 405) was approximately 6% lower compared to male patients of the same body weight (N = 642). In rosiglitazone and metformin combination trials, efficacy was demonstrated with no gender differences in glycemic response.

Metformin pharmacokinetic parameters did not differ significantly between normal subjects and patients with type 2 diabetes when analyzed according to gender (males = 19, females = 16). Similarly, in controlled clinical trials in patients with type 2 diabetes, the antihyperglycemic effect of metformin tablets was comparable in males and females.

Race: Results of a population pharmacokinetic analysis including subjects of white, black, and other ethnic origins indicate that race has no influence on the pharmacokinetics of rosiglitazone.

No trials of metformin pharmacokinetic parameters according to race have been performed. In controlled clinical trials of metformin in patients with type 2 diabetes, the antihyperglycemic effect was comparable in whites (N = 249), blacks (N = 51), and Hispanics (N = 24).

Pediatric: No pharmacokinetic data from trials in pediatric subjects are available for AVANDAMET.

12.4 Drug-Drug Interactions

Rosiglitazone: Drugs That Inhibit, Induce, or are Metabolized by Cytochrome P450: In vitro drug metabolism studies suggest that rosiglitazone does not inhibit any of the major P450 enzymes at clinically relevant concentrations. In vitro data demonstrate that rosiglitazone is predominantly metabolized by CYP2C8, and to a lesser extent, 2C9. [See Drug Interactions (7.1).]

Rosiglitazone (4 mg twice daily) was shown to have no clinically relevant effect on the pharmacokinetics of nifedipine and oral contraceptives (ethinyl estradiol and norethindrone), which are predominantly metabolized by CYP3A4.

Gemfibrozil: Concomitant administration of gemfibrozil (600 mg twice daily), an inhibitor of CYP2C8, and rosiglitazone (4 mg once daily) for 7 days increased rosiglitazone AUC by 127%, compared to the administration of rosiglitazone (4 mg once daily) alone. Given the potential for dose-related adverse events with rosiglitazone, a decrease in the dose of rosiglitazone may be needed when gemfibrozil is introduced. [See Drug Interactions (7.1).]

Rifampin: Rifampin administration (600 mg once a day), an inducer of CYP2C8, for 6 days is reported to decrease rosiglitazone AUC by 66%, compared to the administration of rosiglitazone (8 mg) alone.^11 [See Drug Interactions (7.1).]

Metformin: Cationic Drugs: Cationic drugs (e.g., amiloride, digoxin, morphine, procainamide, quinidine, quinine, ranitidine, triamterene, trimethoprim, and vancomycin) that are eliminated by renal tubular secretion theoretically have the potential for interaction with metformin by competing for common renal tubular transport systems. Such interaction between metformin and oral cimetidine has been observed in normal healthy volunteers in both single- and multiple-dose, metformin-cimetidine drug interaction trials, with a 60% increase in peak metformin plasma and whole blood concentrations and a 40% increase in plasma and whole blood metformin AUC. There was no change in elimination half-life in the single-dose trial. Metformin had no effect on cimetidine pharmacokinetics. [See Warnings and Precautions (5.1) and Drug Interactions (7.2).]

Furosemide: A single-dose, metformin-furosemide drug interaction trial in healthy subjects demonstrated that pharmacokinetic parameters of both compounds were affected by coadministration. Furosemide increased the metformin plasma and blood Cmax by 22% and blood AUC by 15%, without any significant change in metformin renal clearance. When administered with metformin, the Cmax and AUC of furosemide were 31% and 12% smaller, respectively, than when administered alone, and the terminal half-life was decreased by 32%, without any significant change in furosemide renal clearance. No information is available about the interaction of metformin and furosemide when coadministered chronically.

Nifedipine: A single-dose, metformin-nifedipine drug interaction trial in normal healthy volunteers demonstrated that coadministration of nifedipine increased plasma metformin Cmax and AUC by 20% and 9%, respectively, and increased the amount excreted in the urine. Tmax and half-life were unaffected. Nifedipine appears to enhance the absorption of metformin. Metformin had minimal effects on nifedipine.

Other: Certain drugs tend to produce hyperglycemia and may lead to loss of glycemic control. These drugs include thiazides and other diuretics, corticosteroids, phenothiazines, thyroid products, estrogens, oral contraceptives, phenytoin, nicotinic acid, sympathomimetics, calcium channel blocking drugs, and isoniazid.

In healthy volunteers, the pharmacokinetics of metformin and propranolol and metformin and ibuprofen were not affected when coadministered in single-dose interaction trials.

Metformin is negligibly bound to plasma proteins and is therefore, less likely to interact with highly protein-bound drugs such as salicylates, sulfonamides, chloramphenicol, and probenecid.

13 NONCLINICAL TOXICOLOGY

13.1 Carcinogenesis, Mutagenesis, Impairment of Fertility

No animal studies have been conducted with AVANDAMET. The following data are based on findings in studies performed with rosiglitazone or metformin individually.

Rosiglitazone: A 2-year carcinogenicity study was conducted in Charles River CD-1 mice at doses of 0.4, 1.5, and 6 mg/kg/day in the diet (highest dose equivalent to approximately 12 times human AUC at the maximum recommended human daily dose of the rosiglitazone component of AVANDAMET). Sprague-Dawley rats were dosed for 2 years by oral gavage at doses of 0.05, 0.3, and 2 mg/kg/day (highest dose equivalent to approximately 10 and 20 times human AUC at the maximum recommended human daily dose of the rosiglitazone component of AVANDAMET for male and female rats, respectively).

Rosiglitazone was not carcinogenic in the mouse. There was an increase in incidence of adipose hyperplasia in the mouse at doses ≥1.5 mg/kg/day (approximately 2 times human AUC at the maximum recommended human daily dose of the rosiglitazone component of AVANDAMET). In rats, there was a significant increase in the incidence of benign adipose tissue tumors (lipomas) at doses ≥0.3 mg/kg/day (approximately 2 times human AUC at the maximum recommended human daily dose of the rosiglitazone component of AVANDAMET). These proliferative changes in both species are considered due to the persistent pharmacological overstimulation of adipose tissue.

Rosiglitazone was not mutagenic or clastogenic in the in vitro bacterial assays for gene mutation, the in vitro chromosome aberration test in human lymphocytes, the in vivo mouse micronucleus test, and the in vivo/in vitro rat UDS assay. There was a small (about 2-fold) increase in mutation in the in vitro mouse lymphoma assay in the presence of metabolic activation.

Rosiglitazone had no effects on mating or fertility of male rats given up to 40 mg/kg/day (approximately 116 times human AUC at the maximum recommended human daily dose of the rosiglitazone component of AVANDAMET). Rosiglitazone altered estrous cyclicity (2 mg/kg/day) and reduced fertility (40 mg/kg/day) of female rats in association with lower plasma levels of progesterone and estradiol (approximately 20 and 200 times human AUC at the maximum recommended human daily dose of the rosiglitazone component of AVANDAMET, respectively). No such effects were noted at 0.2 mg/kg/day (approximately 3 times human AUC at the maximum recommended human daily dose of the rosiglitazone component of AVANDAMET). In juvenile rats dosed from 27 days of age through to sexual maturity (at up to 40 mg/kg/day), there was no effect on male reproductive performance, or on estrous cyclicity, mating performance or pregnancy incidence in females (approximately 68 times human AUC at the maximum recommended daily dose of rosiglitazone). In monkeys, rosiglitazone (0.6 and 4.6 mg/kg/day; approximately 3 and 15 times human AUC at the maximum recommended human daily dose of the rosiglitazone component of AVANDAMET, respectively) diminished the follicular phase rise in serum estradiol with consequential reduction in the luteinizing hormone surge, lower luteal phase progesterone levels, and amenorrhea. The mechanism for these effects appears to be direct inhibition of ovarian steroidogenesis.

Metformin: Long-term carcinogenicity studies have been performed in rats (dosing duration of 104 weeks) and mice (dosing duration of 91 weeks) at doses up to and including 900 mg/kg/day and 1,500 mg/kg/day, respectively. These doses are both approximately 4 times the maximum recommended human daily dose of 2,000 mg of the metformin component of AVANDAMET based on body surface area comparisons. No evidence of carcinogenicity with metformin was found in either male or female mice. Similarly, there was no tumorigenic potential observed with metformin in male rats. There was, however, an increased incidence of benign stromal uterine polyps in female rats treated with 900 mg/kg/day.

There was no evidence of mutagenic potential of metformin in the following in vitro tests: Ames test (S. typhimurium), gene mutation test (mouse lymphoma cells), or chromosomal aberrations test (human lymphocytes). Results in the in vivo mouse micronucleus test were also negative.

Fertility of male or female rats was unaffected by metformin when administrated at doses as high as 600 mg/kg/day, which is approximately 3 times the maximum recommended human daily dose of the metformin component of AVANDAMET based on body surface area comparisons.

13.2 Animal Toxicology

Heart weights were increased in mice (3 mg/kg/day), rats (5 mg/kg/day), and dogs (2 mg/kg/day) with rosiglitazone treatments (approximately 5, 22, and 2 times human AUC at the maximum recommended human daily dose of the rosiglitazone component of AVANDAMET, respectively). Effects in juvenile rats were consistent with those seen in adults. Morphometric measurement indicated that there was hypertrophy in cardiac ventricular tissues, which may be due to increased heart work as a result of plasma volume expansion.

14 CLINICAL STUDIES

AVANDAMET was not studied in patients previously treated with metformin monotherapy; however, the combination of rosiglitazone and metformin was compared to rosiglitazone and metformin monotherapies in clinical trials. Bioequivalence between AVANDAMET and coadministered rosiglitazone tablets and metformin tablets has been demonstrated [see Clinical Pharmacology (12.3)].

A total of 670 patients with type 2 diabetes participated in two 26-week, randomized, double-blind, placebo/active-controlled trials designed to assess the efficacy of rosiglitazone in combination with metformin. Rosiglitazone, administered in either once-daily or twice-daily dosing regimens, was added to the therapy of patients who were inadequately controlled on 2.5 grams/day of metformin.

In one trial, patients inadequately controlled on 2.5 grams/day of metformin (mean baseline FPG 216 mg/dL and mean baseline HbA1c 8.8%) were randomized to receive rosiglitazone 4 mg once daily, rosiglitazone 8 mg once daily, or placebo in addition to metformin. A statistically significant improvement in FPG and HbA1c was observed in patients treated with the combinations of metformin and rosiglitazone 4 mg once daily and rosiglitazone 8 mg once daily, versus patients continued on metformin alone (see Table 11).

Table 11. Glycemic Parameters in a 26-Week Trial of Rosiglitazone Added to Metformin Therapy
 | Metformin | Rosiglitazone; 4 mg once daily + metformin | Rosiglitazone; 8 mg once daily + metformin
N | 113 | 116 | 110
FPG (mg/dL)
Baseline (mean) | 214 | 215 | 220
Change from baseline (mean) | 6 | -33 | -48
Difference from metformin alone (adjusted mean) |  | -40a | -53a
% of patients with ≥30 mg/dL decrease from baseline | 20% | 45% | 61%
HbA1c (%)
Baseline (mean) | 8.6 | 8.9 | 8.9
Change from baseline (mean) | 0.5 | -0.6 | -0.8
Difference from metformin alone (adjusted mean) |  | -1.0a | -1.2a
% of patients with HbA1c ≥0.7% decrease from baseline | 11% | 45% | 52%

a P <0.0001 compared to metformin.

In a second 26-week trial, patients with type 2 diabetes inadequately controlled on 2.5 grams/day of metformin who were randomized to receive the combination of rosiglitazone 4 mg twice daily and metformin (N = 105) showed a statistically significant improvement in glycemic control with a mean treatment effect for FPG of -56 mg/dL and a mean treatment effect for HbA1c of -0.8% over metformin alone. The combination of metformin and rosiglitazone resulted in lower levels of FPG and HbA1c than either agent alone.

15 REFERENCES

1. Food and Drug Administration Briefing Document. Joint meeting of the Endocrinologic and Metabolic Drugs and Drug Safety and Risk Management Advisory Committees. July 13-14, 2010.
2. Winkelmayer WC, et al. Comparison of cardiovascular outcomes in elderly patients with diabetes who initiated rosiglitazone vs pioglitazone therapy. Arch Intern Med 2008;168(21):2368-2375.
3. Juurlink DN, et al. Adverse cardiovascular events during treatment with pioglitazone and rosiglitazone: population based cohort study. BMJ 2009; 339.
4. Graham DJ, et al. Risk of acute myocardial infarction, stroke, heart failure, and death in elderly medicare patients treated with rosiglitazone or pioglitazone. JAMA 2010;304:411-418.
5. Wertz DA, et al. Risk of cardiovascular events and all-cause mortality in patients with Thiazolidinediones in a managed-care population. Circ Cardiovasc Qual Outcomes 2010;3: 538-545.
6. DREAM Trial Investigators. Effect of rosiglitazone on the frequency of diabetes in patients with impaired glucose tolerance or impaired fasting glucose: a randomised controlled trial. Lancet 2006;368:1096-1105.
7. Kahn S, et al. Glycemic durability of rosiglitazone, metformin or glyburide monotherapy. New England Journal of Medicine 2006, 355:2427-2443.
8. Home P, et al. Rosiglitazone evaluated for cardiovascular outcomes in oral agent combination therapy for type 2 diabetes (RECORD): a multicenter, randomized, open-label trial. Lancet 2009, 373:2125-35.
9. Dormandy J et al. Secondary prevention of macrovascular events in patients with type 2 diabetes in the PROactive study (Prospective Pioglitazone Clinical Trial in Macrovascular Events): a randomized controlled trial. Lancet 2005, 366:1279-89.
10. Bilik D, et al. Thiazolidinediones, cardiovascular disease and cardiovascular mortality: translating research into action for diabetes (TRIAD). Pharmocoepidemiol Drug Saf 2010; 19: 715–721.
11. Park JY, Kim KA, Kang MH, et al. Effect of rifampin on the pharmacokinetics of rosiglitazone in healthy subjects. Clin Pharmacol Ther 2004;75:157-162.

16 HOW SUPPLIED/STORAGE AND HANDLING

Each film-coated oval tablet contains rosiglitazone as the maleate and metformin hydrochloride as follows:

2 mg/500 mg – pale pink, tablet, debossed with gsk on one side and 2/500 on the other.

4 mg/500 mg – orange, tablet, debossed with gsk on one side and 4/500 on the other.

2 mg/1,000 mg – yellow, tablet, debossed with gsk on one side and 2/1000 on the other.

4 mg/1,000 mg – pink, tablet, debossed with gsk on one side and 4/1000 on the other.

2 mg/500 mg
Bottles of 20 | NDC 54868-4965-1
Bottles of 30 | NDC 54868-4965-2
Bottles of 60 | NDC 54868-4965-0
4 mg/500 mg
Bottles of 60 | NDC 54868-5157-0
2 mg/1,000 mg
Bottles of 60 | NDC 54868-5376-0

Store at 25°C (77°F); excursions permitted to 15° to 30°C (59° to 86°F). Dispense in a tight, light-resistant container.

17 PATIENT COUNSELING INFORMATION

See Medication Guide.

17.1 Patient Advice

There are multiple medications available to treat type 2 diabetes. The benefits and risks of each available diabetes medication should be taken into account when choosing a particular diabetes medication for a given patient.

Patients should be informed of the risks and benefits of AVANDAMET. AVANDAMET should only be taken by adults with type 2 diabetes who are already taking rosiglitazone, or who are not already taking rosiglitazone and are unable to achieve adequate glycemic control on other diabetes medications, and, in consultation with their healthcare provider, have decided not to take pioglitazone (ACTOS) or pioglitazone-containing medications (ACTOPLUS MET, ACTOPLUS MET XR, DUETACT) for medical reasons.

Patients should be informed of the following:

- The risks of lactic acidosis, its symptoms, and conditions that predispose to its development, as noted in the WARNINGS and PRECAUTIONS sections, should be explained to patients. Patients should be advised to discontinue AVANDAMET immediately and to promptly notify their health practitioner if unexplained hyperventilation, myalgia, malaise, unusual somnolence, or other nonspecific symptoms occur. Once a patient is stabilized on any dose level of AVANDAMET, gastrointestinal symptoms, which are common during initiation of metformin therapy, are unlikely to be drug related. Later occurrence of gastrointestinal symptoms could be due to lactic acidosis or other serious disease.
- Avoid excessive alcohol intake, either acute or chronic, while receiving AVANDAMET.
- AVANDAMET is not recommended for patients with symptomatic heart failure.
- Results of a set of clinical trials suggest that treatment with AVANDAMET is associated with an increased risk for myocardial infarction (heart attack), especially in patients taking insulin. Clinical trials have not shown any difference between rosiglitazone and comparator medications in overall mortality or CV-related mortality.
- AVANDAMET is not recommended for patients who are taking insulin.
- Management of type 2 diabetes should include diet control. Caloric restriction, weight loss, and exercise are essential for the proper treatment of the diabetic patient because they help improve insulin sensitivity. This is important not only in the primary treatment of type 2 diabetes but also in maintaining the efficacy of drug therapy.
- It is important to adhere to dietary instructions and to regularly have blood glucose, glycosylated hemoglobin (HbA1c), renal function, and hematologic parameters tested. It can take 2 weeks to see a reduction in blood glucose and 2 to 3 months to see the full effect of AVANDAMET.
- Blood will be drawn to check their liver function prior to the start of therapy and periodically thereafter per the clinical judgment of the healthcare professional. Patients with unexplained symptoms of nausea, vomiting, abdominal pain, fatigue, anorexia, or dark urine should immediately report these symptoms to their physician.
- Patients who experience an unusually rapid increase in weight or edema or who develop shortness of breath or other symptoms of heart failure while on AVANDAMET should immediately report these symptoms to their physician.
- Therapy with AVANDAMET, like other thiazolidinediones, may result in ovulation in some premenopausal anovulatory women. As a result, these patients may be at an increased risk for pregnancy while taking AVANDAMET. Thus, adequate contraception in premenopausal women should be recommended. This possible effect has not been specifically investigated in clinical trials so the frequency of this occurrence is not known.

AVANDAMET is a registered trademark of GlaxoSmithKline.

GLUCOPHAGE is a registered trademark of Merck Santé S.A.S. (an associate of Merck KGaA of Darmstadt, Germany; licensed to Bristol-Myers Squibb Company). ACTOS, ACTOPLUS MET, ACTOPLUS MET XR, and DUETACT are registered trademarks of Takeda Pharmaceutical Company Limited.

GlaxoSmithKline

Research Triangle Park, NC 27709

©2011, GlaxoSmithKline. All rights reserved.

February 2011

AVM:19PI

Relabeling and Repackaging by:
Physicians Total Care, Inc.
Tulsa, Oklahoma 74146

MEDICATION GUIDE

AVANDAMET® (ah-VAN-duh-met)

(rosiglitazone maleate and metformin hydrochloride) Tablets

Read this Medication Guide carefully before you start taking AVANDAMET and each time you get a refill. There may be new information. This information does not take the place of talking with your doctor about your medical condition or your treatment. If you have any questions about AVANDAMET, ask your doctor or pharmacist.

What is the most important information I should know about AVANDAMET?

AVANDAMET may cause serious side effects, including:

New or worse heart failure

- Rosiglitazone, one of the medicines in AVANDAMET, can cause your body to keep extra fluid (fluid retention), which leads to swelling (edema) and weight gain. Extra body fluid can make some heart problems worse or lead to heart failure. Heart failure means your heart does not pump blood well enough.
- If you have severe heart failure, you cannot start AVANDAMET.
- If you have heart failure with symptoms (such as shortness of breath or swelling), even if these symptoms are not severe, AVANDAMET may not be right for you.

Call your doctor right away if you have any of the following:

- swelling or fluid retention, especially in the ankles or legs
- shortness of breath or trouble breathing, especially when you lie down
- an unusually fast increase in weight
- unusual tiredness

Myocardial Infarction (“Heart Attack”)

Rosiglitazone, one of the medicines in AVANDAMET, may raise the risk of heart attack. The risk of having a heart attack may be higher in people who take AVANDAMET with insulin. Most people who take insulin should not also take AVANDAMET.

Symptoms of a heart attack can include the following:

- chest discomfort in the center of your chest that lasts for more than a few minutes, or that goes away or comes back
- chest discomfort that feels like uncomfortable pressure, squeezing, fullness or pain
- pain or discomfort in your arms, back, neck, jaw or stomach
- shortness of breath with or without chest discomfort
- breaking out in a cold sweat
- nausea or vomiting
- feeling lightheaded

Call your doctor or go to the nearest hospital emergency room right away if you think you are having a heart attack.

People with diabetes have a greater risk for heart problems. It is important to work with your doctor to manage other conditions, such as high blood pressure or high cholesterol.

Lactic acidosis

Metformin, one of the medicines in AVANDAMET, can cause a rare but serious condition called lactic acidosis (a build-up of an acid in the blood) that can cause death. Lactic acidosis is a medical emergency and must be treated in the hospital.

Most people who have had lactic acidosis with metformin have other things that, combined with the metformin, led to the lactic acidosis. Tell your doctor if you have any of the following, because you have a higher chance for getting lactic acidosis with AVANDAMET if you:

- have kidney problems or your kidneys are affected by certain X-ray tests that use injectable dye. People with kidney problems should not take AVANDAMET.
- have liver problems
- drink alcohol very often, or drink a lot of alcohol in short-term "binge" drinking
- get dehydrated (lose a large amount of body fluids). This can happen if you are sick with a fever, vomiting or diarrhea. Dehydration can also happen when you sweat a lot with activity or exercise and do not drink enough fluids.
- have surgery
- have a heart attack, severe infection, or stroke
- are 80 years of age or older, and your kidneys are not working properly

The best way to keep from having a problem with lactic acidosis from metformin is to tell your doctor if you have any of the problems in the list above. Your doctor may decide to stop your AVANDAMET for a while if you have any of these things.

Lactic acidosis can be hard to diagnose early, because the early symptoms could seem like the symptoms of many other health problems besides lactic acidosis. You should call your doctor right away if you get the following symptoms, which could be signs of lactic acidosis:

- you feel very weak or tired
- you have unusual (not normal) muscle pain
- you have stomach pains
- you have trouble breathing
- you feel dizzy or lightheaded
- you have a slow or irregular heartbeat

AVANDAMET can have other serious side effects. Be sure to read the section below “What are possible side effects of AVANDAMET?”.

What is AVANDAMET?

AVANDAMET contains two prescription medicines for treating diabetes, rosiglitazone maleate (AVANDIA) and metformin hydrochloride. AVANDAMET is used, with diet and exercise, to treat certain adults with type 2 (“adult-onset” or “non-insulin dependent”) diabetes (“high blood sugar”) who are:

- already taking rosiglitazone or rosiglitazone-containing products
- unable to control their blood sugar on other diabetes medicines, and after talking with their doctor have decided not to take pioglitazone (ACTOS) or pioglitazone-containing products (ACTOPLUS MET, ACTOPLUS MET XR, DUETACT)

Metformin works mainly by decreasing the production of sugar by your liver. Rosiglitazone helps your body respond better to its natural insulin and does not cause your body to make more insulin. These medicines work together to help control your blood sugar. AVANDAMET may be used alone or with other diabetes medicines.

AVANDAMET is not for people with type 1 diabetes mellitus or to treat a condition called diabetic ketoacidosis.

It is not known if AVANDAMET is safe and effective in children under 18 years old.

Who should not take AVANDAMET?

Do not take AVANDAMET if you:

- have kidney problems. Before you take AVANDAMET and while you take it, your doctor should test your blood to check for signs of kidney problems.
- have a condition known as metabolic acidosis, including diabetic ketoacidosis.
- are going to have an x-ray procedure with an injection of dyes (contrast agents) in your vein with a needle. Talk to your doctor about when to stop AVANDAMET and when to start it again.

Many people with heart failure should not start taking AVANDAMET. See “What should I tell my doctor before taking AVANDAMET?”.

What should I tell my doctor before taking AVANDAMET?

Before starting AVANDAMET, ask your doctor about what the choices are for diabetes medicines, and what the expected benefits and possible risks are for you in particular.

Before taking AVANDAMET, tell your doctor about all your medical conditions, including if you:

- have heart problems or heart failure
- have kidney problems
- have type 1 (“juvenile”) diabetes or had diabetic ketoacidosis. These conditions should be treated with insulin.
- are going to have dye injected into a vein for an X-ray, CAT scan, heart study, or other type of scanning
- drink a lot of alcohol (all the time or short binge drinking).
- develop a serious condition such as a heart attack, severe infection, or a stroke.
- are 80 years old or older. People who are over 80 years old should not take AVANDAMET unless their kidney function is checked and it is normal.
- have a type of diabetic eye disease called macular edema (swelling of the back of the eye).
- have liver problems. Your doctor should do blood tests to check your liver before you start taking AVANDAMET and during treatment as needed.
- had liver problems while taking REZULIN® (troglitazone), another medicine for diabetes.
- are pregnant or plan to become pregnant. AVANDAMET should not be used during pregnancy. It is not known if AVANDAMET can harm your unborn baby. You and your doctor should talk about the best way to control your diabetes during pregnancy. If you are a premenopausal woman (before the “change of life”) who does not have regular monthly periods, AVANDAMET may increase your chances of becoming pregnant. Talk to your doctor about birth control choices while taking AVANDAMET. Tell your doctor right away if you become pregnant while taking AVANDAMET.
- are breast-feeding or planning to breast-feed. It is not known if AVANDAMET passes into breast milk. You should not use AVANDAMET while breast-feeding.

Tell your doctor about all the medicines you take including prescription and non-prescription medicines, vitamins or herbal supplements. AVANDAMET and certain other medicines can affect each other and may lead to serious side effects including high or low blood sugar, or heart problems. Your doctor may need to change your dose of AVANDAMET or your other medicines. Especially tell your doctor if you take:

- insulin.
- any medicines for high blood pressure, high cholesterol or heart failure, or for prevention of heart disease or stroke.

Know the medicines you take. Keep a list of all your medicines and show it to your doctor and pharmacist before you start a new medicine. They will tell you if it is alright to take AVANDAMET with other medicines.

How should I take AVANDAMET?

- Take AVANDAMET exactly as prescribed. Your doctor may need to change your dose until your blood sugar is better controlled.
- AVANDAMET should be taken by mouth and with meals.
- AVANDAMET may be prescribed alone or with other diabetes medicines. This will depend on how well your blood sugar is controlled.
- It can take 2 weeks for AVANDAMET to start lowering your blood sugar. It may take 2 to 3 months to see the full effect on your blood sugar level.
- If you miss a dose of AVANDAMET, take it as soon as you remember, unless it is time to take your next dose. Take your next dose at the usual time. Do not take double doses to make up for a missed dose.
- If you take too much AVANDAMET, call your doctor or poison control center right away.
- Test your blood sugar regularly as your doctor tells you.
- Diet and exercise can help your body use its blood sugar better. It is important to stay on your recommended diet, lose extra weight, and get regular exercise while taking AVANDAMET.
- Your doctor should do blood tests to check your liver and kidneys before you start AVANDAMET and during treatment as needed. Your doctor should also do regular blood sugar tests (for example, “A1C”) to monitor your response to AVANDAMET.

There may be times when you will need to stop taking AVANDAMET for a short time. Tell your doctor if you:

- are sick with severe vomiting, diarrhea or fever, or if you drink a much lower amount of liquid than normal.
- are going to have dye injected into a vein for an X-ray, CAT scan, heart study or other type of scanning.
- plan to have surgery.

What should I avoid while taking AVANDAMET?

Do not drink a lot of alcohol while taking AVANDAMET. This means you should not “binge drink”, and you should not drink a lot of alcohol on a regular basis. Drinking a lot of alcohol can increase the chance of getting lactic acidosis.

What are possible side effects of AVANDAMET?

AVANDAMET may cause serious side effects, including:

- New or worse heart failure. See “What is the most important information I should know about AVANDAMET?”.
- Heart attack. See “What is the most important information I should know about AVANDAMET?”.
- Swelling (edema). AVANDAMET can cause swelling due to fluid retention. See “What is the most important information I should know about AVANDAMET?”.
- Weight gain. Rosiglitazone, one of the medicines in AVANDAMET, can cause weight gain that may be due to fluid retention or extra body fat. Metformin, the other medicine in AVANDAMET, can cause weight loss. There is little change in weight with AVANDAMET. Weight gain can be a serious problem for people with certain conditions including heart problems. See “What is the most important information I should know about AVANDAMET?”
- Liver problems. It is important for your liver to be working normally when you take AVANDAMET. Your doctor should do blood tests to check your liver before you start taking AVANDAMET and during treatment as needed. Call your doctor right away if you have unexplained symptoms such as:
  - nausea or vomiting
  - stomach pain
  - unusual or unexplained tiredness
  - loss of appetite
  - dark urine
  - yellowing of your skin or the whites of your eyes.
- Macular edema (a diabetic eye disease with swelling in the back of the eye). Tell your doctor right away if you have any changes in your vision. Your doctor should check your eyes regularly. Very rarely, some people have had vision changes due to swelling in the back of the eye while taking rosiglitazone, one of the medicines in AVANDAMET.
- Fractures (broken bones), usually in the hand, upper arm or foot. Talk to your doctor for advice on how to keep your bones healthy.
- Low red blood cell count (anemia).
- Low blood sugar (hypoglycemia). Lightheadedness, dizziness, shakiness or hunger may mean that your blood sugar is too low. This can happen if you skip meals, if you use another medicine that lowers blood sugar, or if you have certain medical problems. Call your doctor if low blood sugar levels are a problem for you.
- Ovulation (release of egg from an ovary in a woman) leading to pregnancy. Ovulation may happen in premenopausal women who do not have regular monthly periods. This can increase the chance of pregnancy. See “What should I tell my doctor before taking AVANDAMET?”.

Common side effects of AVANDAMET include:

- Diarrhea, nausea, and upset stomach. These side effects usually happen during the first few weeks of treatment. Taking AVANDAMET with food can help lessen these side effects. If you have unusual or unexpected stomach problems, talk with your doctor. Stomach problems that start up later during treatment with AVANDAMET may be a sign of something more serious and should be discussed with your doctor.
- Cold-like symptoms
- Headache
- Joint aches
- Dizziness

Call your doctor for medical advice about side effects. You may report side effects to FDA at 1-800-FDA-1088.

How should I store AVANDAMET?

- Store AVANDAMET at room temperature, 59° to 86°F (15° to 30°C).
- Keep AVANDAMET in the container it comes in. Keep the container closed tightly.
- Safely, throw away AVANDAMET that is out of date or no longer needed.

Keep AVANDAMET and all medicines out of the reach of children.

General information about AVANDAMET

Medicines are sometimes prescribed for purposes other than those listed in a Medication Guide. Do not use AVANDAMET for a condition for which it was not prescribed. Do not give AVANDAMET to other people, even if they have the same symptoms you have. It may harm them.

This Medication Guide summarizes important information about AVANDAMET. If you would like more information, talk with your doctor. You can ask your doctor or pharmacist for information about AVANDAMET that is written for healthcare professionals. You can also find out more about AVANDAMET by calling 1-888-825-5249.

What are the ingredients in AVANDAMET?

Active Ingredients: Rosiglitazone maleate and metformin hydrochloride

Inactive Ingredients: Hypromellose 2910, lactose monohydrate, magnesium stearate, microcrystalline cellulose, polyethylene glycol 400, povidone 29-32, sodium starch glycolate, titanium dioxide, and 1 or more of the following: Red and yellow iron oxides.

Always check to make sure that the medicine you are taking is the correct one. AVANDAMET tablets are oval and look like this:

- 2 mg/500 mg – pale pink, with “gsk” on one side and “2/500” on the other.
- 4 mg/500 mg – orange, with “gsk” on one side and “4/500” on the other
- 2 mg/1,000 mg – yellow, with “gsk” on one side and “2/1000” on the other
- 4 mg/1,000 mg – pink, with “gsk” on one side and “4/1000” on the other

AVANDAMET is a registered trademark of GlaxoSmithKline.

The other brands listed are trademarks of their respective owners and are not trademarks of GlaxoSmithKline. The makers of these brands are not affiliated with and do not endorse GlaxoSmithKline or its products.

This Medication Guide has been approved by the U.S. Food and Drug Administration.

GlaxoSmithKline

Research Triangle Park, NC 27709

©2011, GlaxoSmithKline. All rights reserved.

February 2011

AVM:3MG

PACKAGE LABEL

Principal Display Panel

Avandamet®

Rosiglitazone maleate/metformin HCl

Tablets

2 mg/500 mg

Rx only

Federal Law requires dispensing of AVANDAMET® with the Medication Guide provided with this Bottle.

Store at 25oC (77oF); excursions permitted to 15oC-30oC (59oF-86oF).

Each tablet contains rosiglitazone maleate equivalent to 2 mg rosiglitazone and 500 mg metformin hydrochloride.

Dispense in a tight, light-resistant container.

Dosage: See accompanying prescribing information.

PACKAGE LABEL

Principal Display Panel

Avandamet®

Rosiglitazone maleate/metformin HCl

Tablets

2 mg/1000 mg

Rx only

Federal Law requires dispensing of AVANDAMET® with the Medication Guide provided with this Bottle.

Store at 25oC (77oF); excursions permitted to 15oC-30oC (59oF-86oF).

Each tablet contains rosiglitazone maleate equivalent to 2 mg rosiglitazone and 1000 mg metformin hydrochloride.

Dispense in a tight, light-resistant container.

Dosage: See accompanying prescribing information.

PACKAGE LABEL

Principal Display Panel

Avandamet®

Rosiglitazone maleate/metformin HCl

Tablets

4 mg/500 mg

60 Tablets

Rx only

Federal Law requires dispensing of AVANDAMET® with the Medication Guide provided with this Bottle.

Store at 25oC (77oF); excursions permitted to 15oC-30oC (59oF-86oF).

Each tablet contains rosiglitazone maleate equivalent to 4 mg rosiglitazone and 500 mg metformin hydrochloride.

Dispense in a tight, light-resistant container.

Dosage: See accompanying prescribing information.

PACKAGE LABEL

Principal Display Panel

Avandamet®

Rosiglitazone maleate/metformin HCl

Tablets

4 mg/1000 mg

60 Tablets

Rx only

Federal Law requires dispensing of AVANDAMET® with the Medication Guide provided with this Bottle.

Store at 25oC (77oF); excursions permitted to 15oC-30oC (59oF-86oF).

Each tablet contains rosiglitazone maleate equivalent to 4 mg rosiglitazone and 1000 mg metformin hydrochloride.

Dispense in a tight, light-resistant container.

Dosage: See accompanying prescribing information.